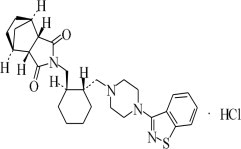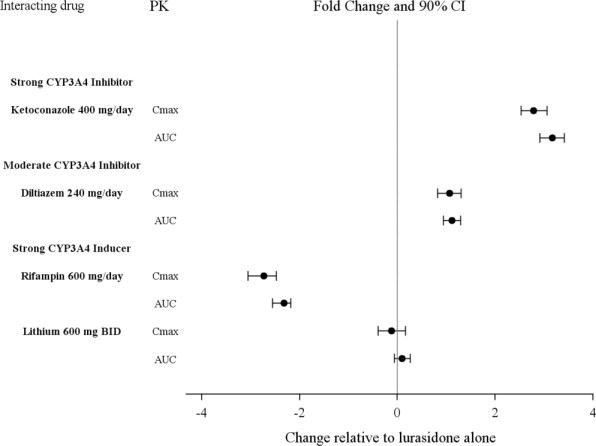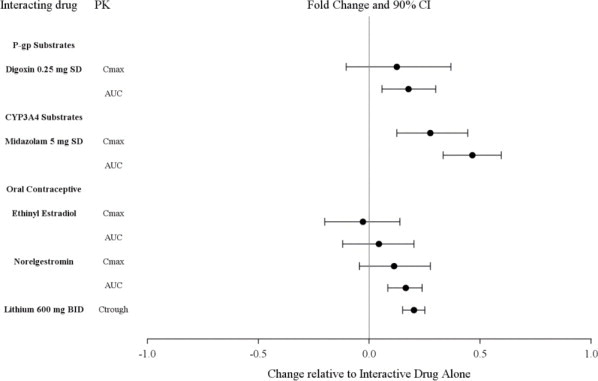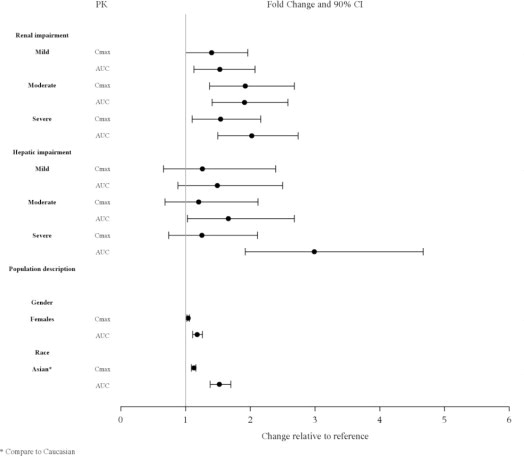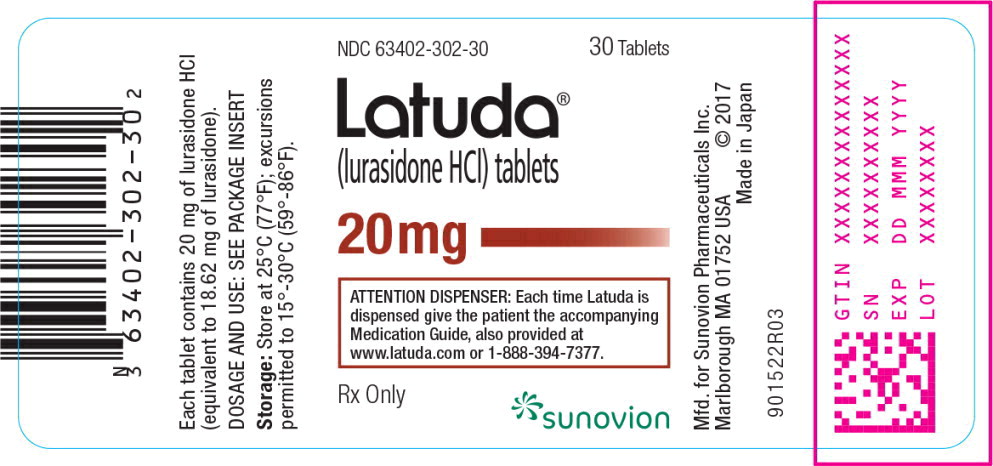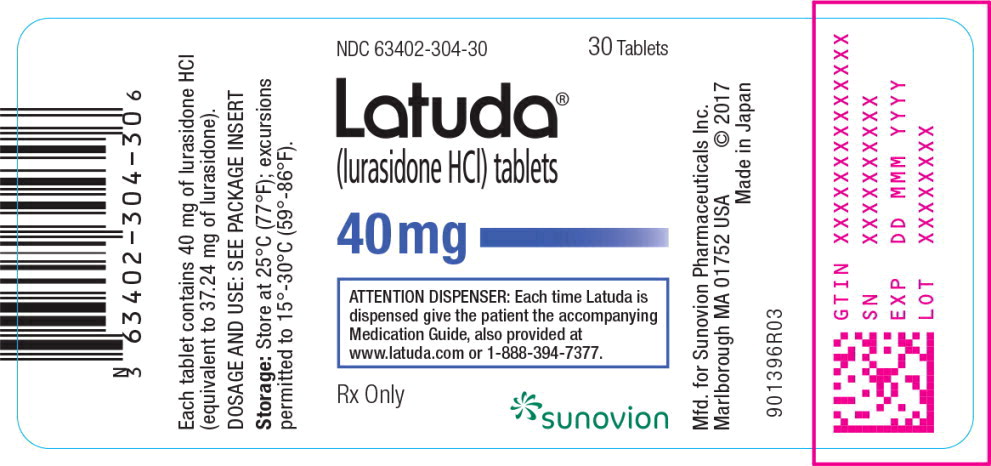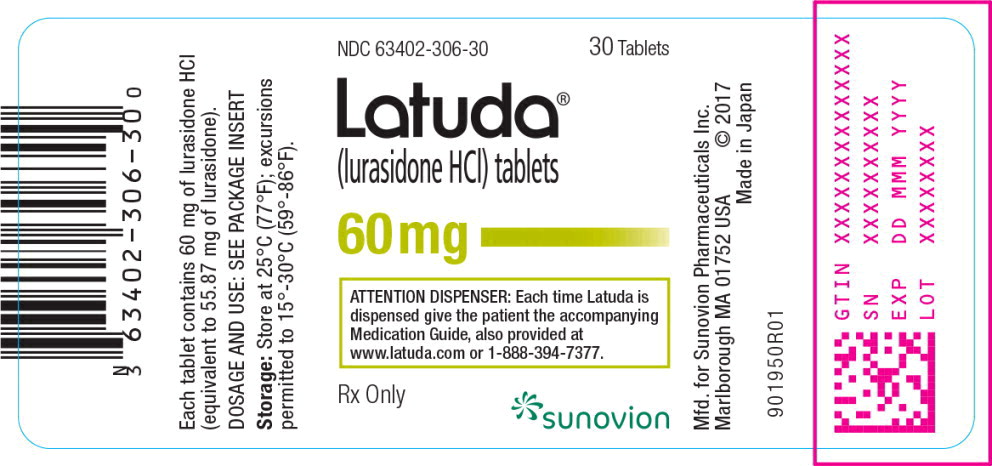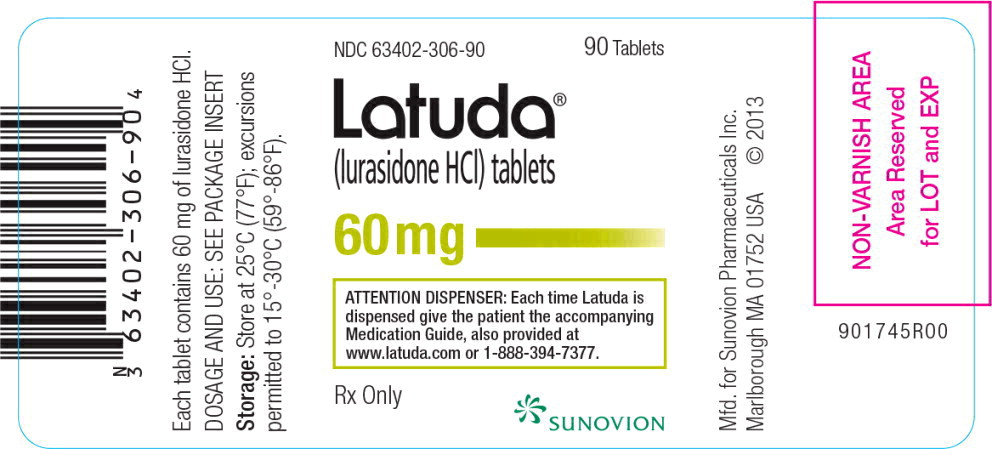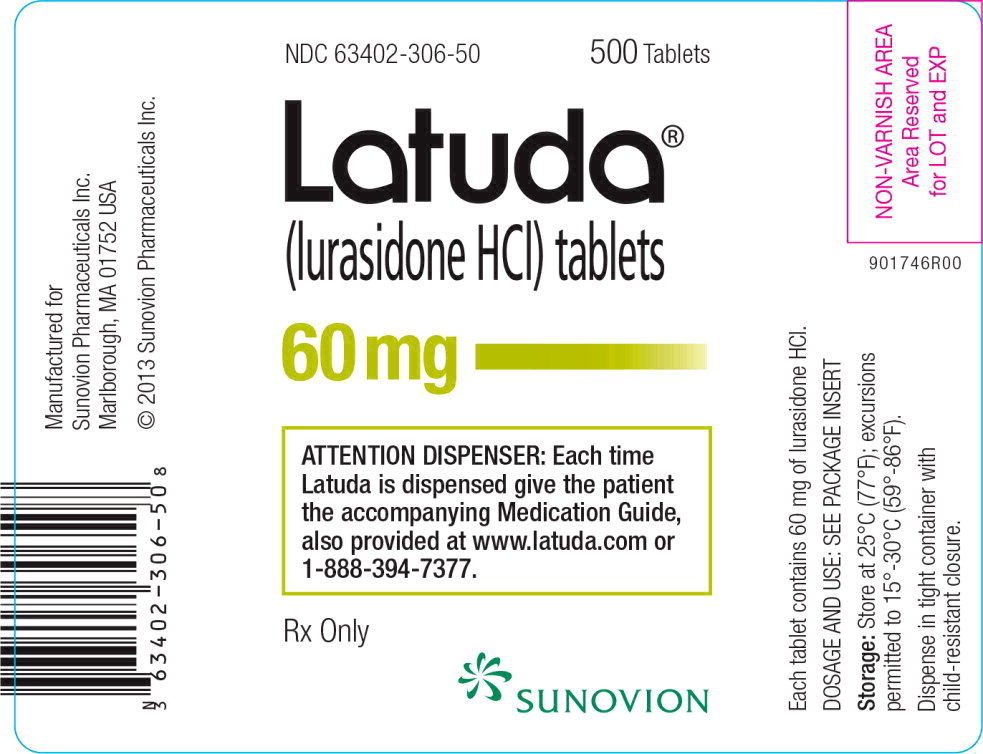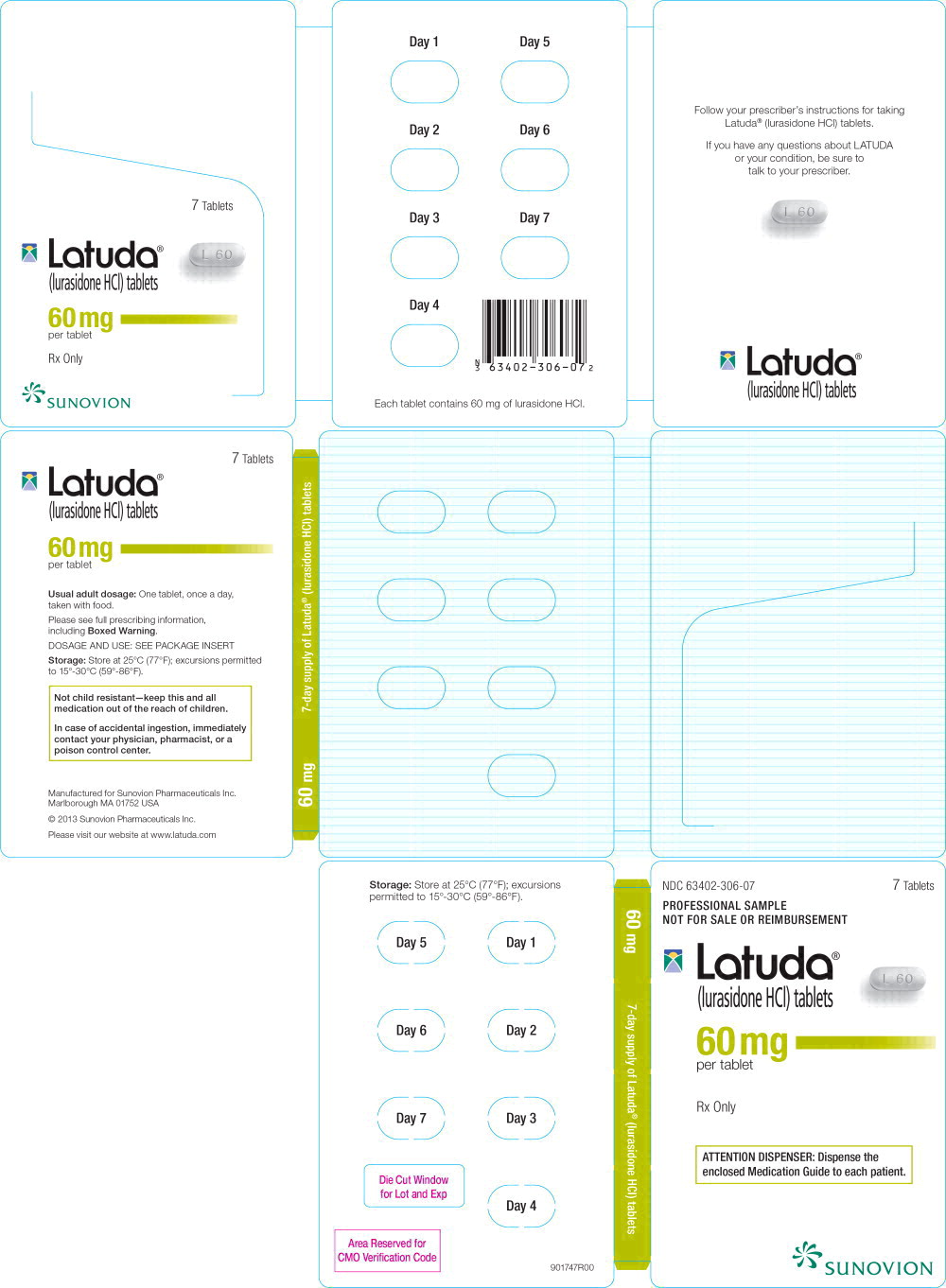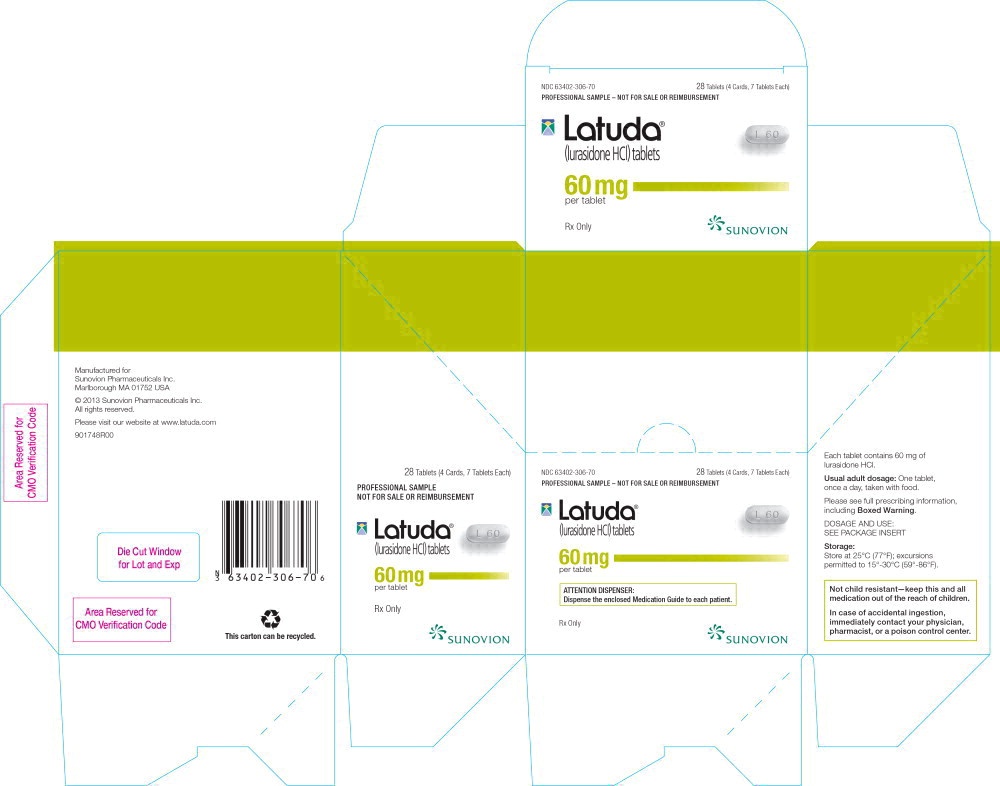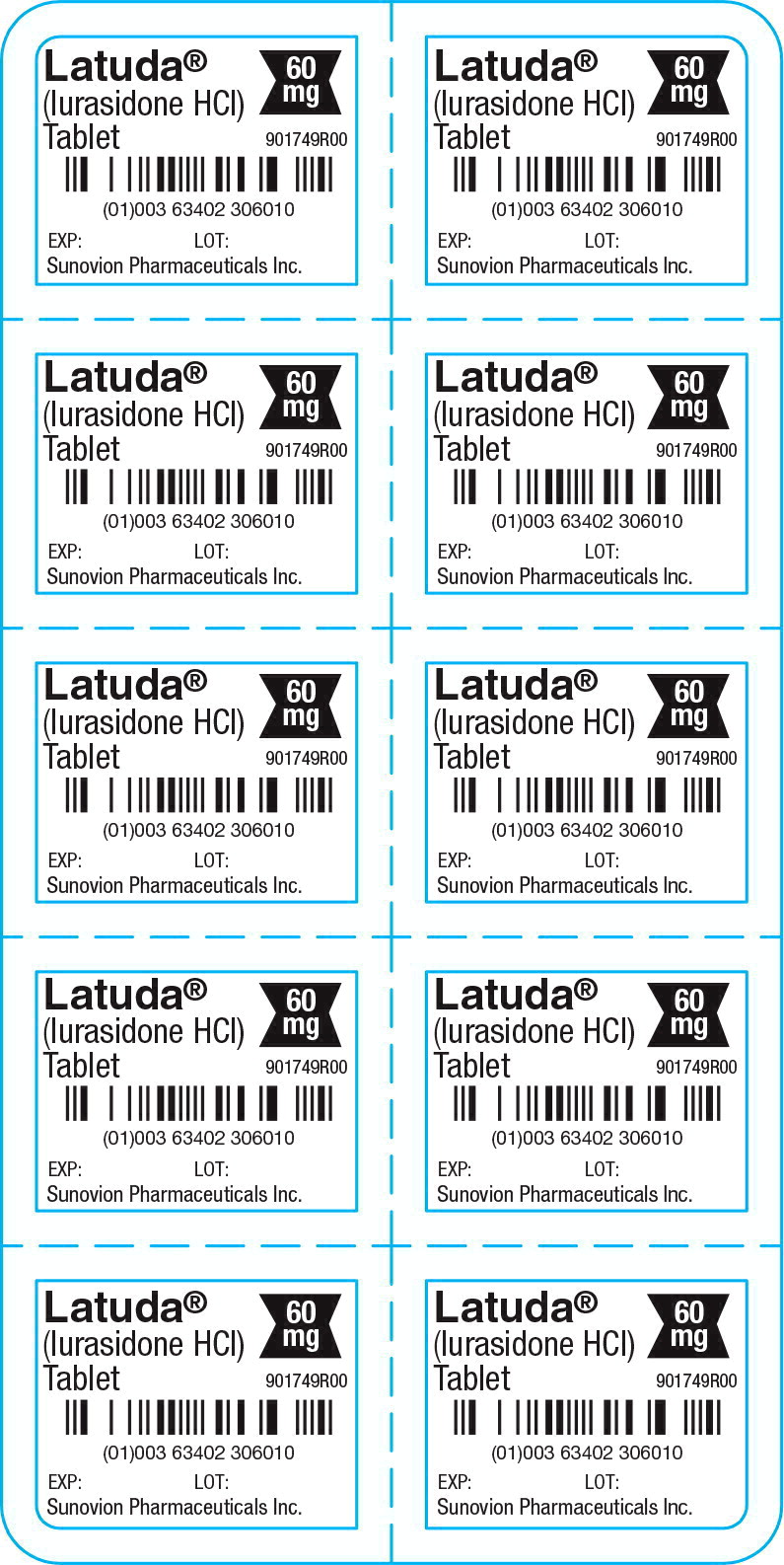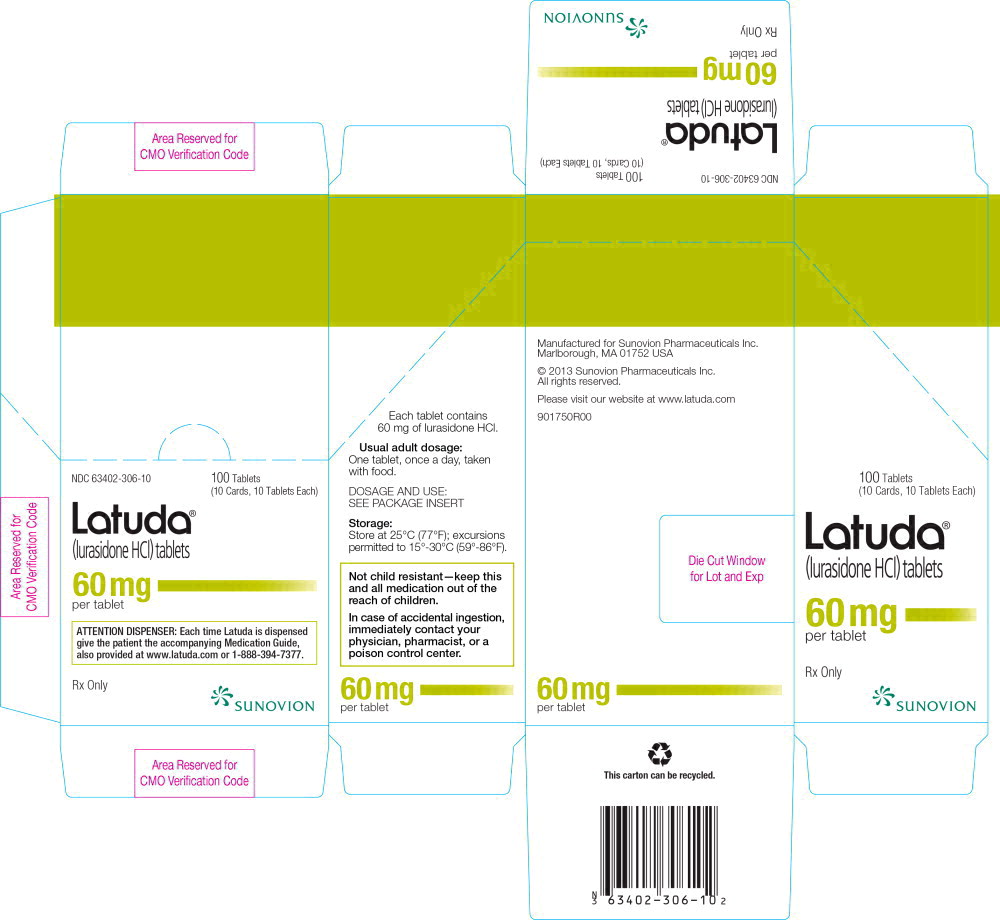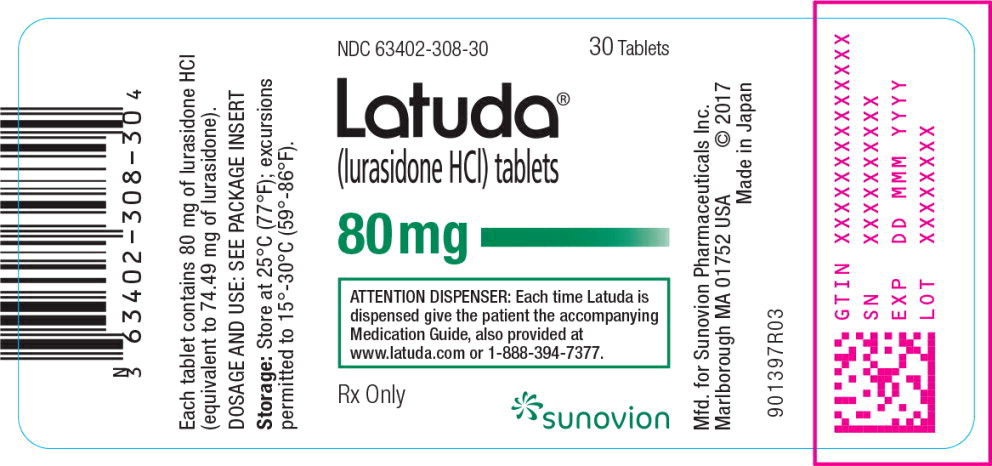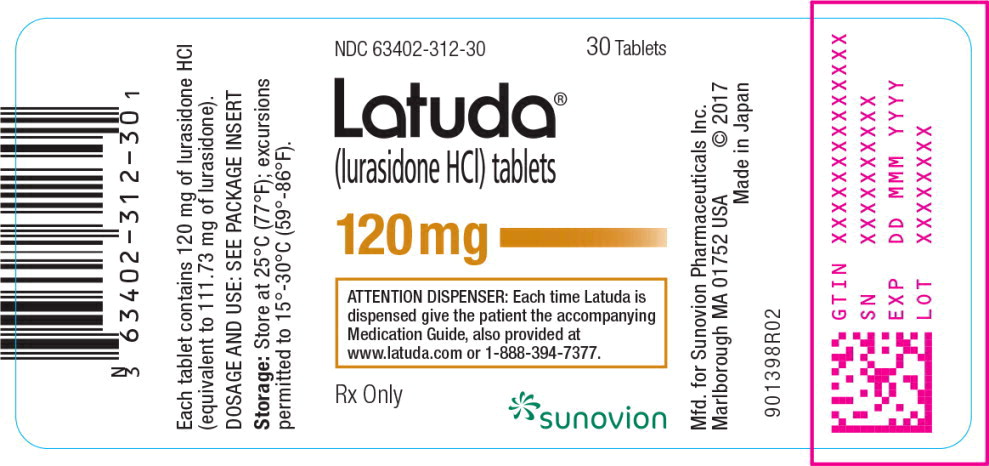 DRUG LABEL: Latuda
NDC: 63402-302 | Form: TABLET, FILM COATED
Manufacturer: Sumitomo Pharma America, Inc.
Category: prescription | Type: HUMAN PRESCRIPTION DRUG LABEL
Date: 20250131

ACTIVE INGREDIENTS: lurasidone hydrochloride 20 mg/1 1
INACTIVE INGREDIENTS: mannitol; starch, corn; croscarmellose sodium; hypromellose 2910 (6 MPA.S); magnesium stearate; Carnauba Wax

HIGHLIGHTS OF PRESCRIBING INFORMATION

These highlights do not include all the information needed to use LATUDA safely and effectively. See full prescribing information for LATUDA.
LATUDA (lurasidone hydrochloride) tablets, for oral use
Initial U.S. Approval: 2010

RECENT MAJOR CHANGES

Warnings and Precautions (5.7) | 1/2025

WARNING: INCREASED MORTALITY IN ELDERLY PATIENTS WITH DEMENTIA-RELATED PSYCHOSIS; and SUICIDAL THOUGHTS AND BEHAVIORS

See full prescribing information for complete boxed warning.

- Elderly patients with dementia-related psychosis treated with antipsychotic drugs are at an increased risk of death. LATUDA is not approved for the treatment of patients with dementia-related psychosis (5.1).
- Antidepressants increased the risk of suicidal thoughts and behavior in pediatric and young adult patients. Closely monitor for clinical worsening and emergence of suicidal thoughts and behaviors (5.2).

1 INDICATIONS AND USAGE

LATUDA is an atypical antipsychotic indicated for the treatment of:

- Schizophrenia in adults and adolescents (13 to 17 years) (1, 14.1)
- Depressive episode associated with Bipolar I Disorder (bipolar depression) in adults and pediatric patients (10 to 17 years) as monotherapy (1, 14.2)
- Depressive episode associated with Bipolar I Disorder (bipolar depression) in adults as adjunctive therapy with lithium or valproate (1, 14.2)

2 DOSAGE AND ADMINISTRATION

LATUDA should be taken with food (at least 350 calories). Administration with food substantially increases the absorption of LATUDA (2.3, 12.3).

Indication | Starting Dose | Recommended Dose
Schizophrenia – adults (2.1) | 40 mg per day | 40 mg to 160 mg per day
Schizophrenia –adolescents (13 to 17 years) (2.1) | 40 mg per day | 40 mg to 80 mg per day
Bipolar Depression - adults (2.2) | 20 mg per day | 20 mg to 120 mg per day
Bipolar Depression –pediatric patients (10 to 17 years) (2.2) | 20 mg per day | 20 mg to 80 mg per day

- Moderate and Severe Renal Impairment: Recommended starting dose is 20 mg per day, and the maximum recommended dose is 80 mg per day (2.4, 8.6).
- Moderate and Severe Hepatic Impairment: Recommended starting dose is 20 mg per day. The maximum recommended dose is 80 mg per day in moderate hepatic impairment and 40 mg per day in severe hepatic impairment (2.5, 8.7).
- Concomitant Use of a Moderate CYP3A4 inhibitor (e.g., diltiazem):
  LATUDA dose should be reduced to half of the original dose level. Recommended starting dose is 20 mg per day. Maximum recommended dose is 80 mg per day (2.6, 7.1).
- Concomitant Use of a Moderate CYP3A4 Inducer:
  It may be necessary to increase the dose of LATUDA (2.6, 7.1).

3 DOSAGE FORMS AND STRENGTHS

Tablets: 20 mg, 40 mg, 60 mg, 80 mg and 120 mg (3)

4 CONTRAINDICATIONS

- Known hypersensitivity to LATUDA or any components in the formulation (4).
- Concomitant use with a strong CYP3A4 inhibitor (e.g., ketoconazole) (2.6, 4, 7.1).
- Concomitant use with a strong CYP3A4 inducer (e.g., rifampin) (2.6, 4, 7.1).

5 WARNINGS AND PRECAUTIONS

- Cerebrovascular Adverse Reactions in Elderly Patients with Dementia-Related Psychosis: Increased incidence of cerebrovascular adverse events (e.g., stroke, transient ischemic attack) (5.3).
- Neuroleptic Malignant Syndrome: Manage with immediate discontinuation and close monitoring (5.4).
- Tardive Dyskinesia: Discontinue if clinically appropriate (5.5).
- Metabolic Changes: Monitor for hyperglycemia/diabetes mellitus, dyslipidemia and weight gain (5.6).
- Hyperprolactinemia: Prolactin elevations may occur (5.7).
- Leukopenia, Neutropenia, and Agranulocytosis: Perform complete blood counts (CBC) in patients with a pre-existing low white blood cell count (WBC) or a history of leukopenia or neutropenia. Consider discontinuing LATUDA if a clinically significant decline in WBC occurs in the absence of other causative factors (5.8).
- Orthostatic Hypotension and Syncope: Monitor heart rate and blood pressure and warn patients with known cardiovascular or cerebrovascular disease, and risk of dehydration or syncope (5.9).

6 ADVERSE REACTIONS

Commonly observed adverse reactions (incidence ≥ 5% and at least twice the rate for placebo) were (6.1):

- Adult patients with schizophrenia: somnolence, akathisia, extrapyramidal symptoms, and nausea
- Adolescent patients (13-17 years) with schizophrenia: somnolence, nausea, akathisia, EPS (non-akathisia), rhinitis (80 mg only), and vomiting
- Adult patients with bipolar depression: akathisia, extrapyramidal symptoms, and somnolence
- Pediatric patients (10-17 years) with bipolar depression: nausea, weight increase, and insomnia.

To report SUSPECTED ADVERSE REACTIONS, Sumitomo Pharma America, Inc. at 1-877-737-7226 or FDA at 1-800-FDA-1088 or www.fda.gov/medwatch.

8 USE IN SPECIFIC POPULATIONS

- Pregnancy: May cause extrapyramidal and or/withdrawal symptoms in neonates with third trimester exposure (8.1).

FULL PRESCRIBING INFORMATION

WARNING: INCREASED MORTALITY IN ELDERLY PATIENTS WITH DEMENTIA-RELATED PSYCHOSIS; and SUICIDAL THOUGHTS AND BEHAVIORS

Increased Mortality in Elderly Patients with Dementia-Related Psychosis

Elderly patients with dementia-related psychosis treated with antipsychotic drugs are at an increased risk of death. LATUDA is not approved for the treatment of patients with dementia-related psychosis [see Warnings and Precautions (5.1)].

Suicidal Thoughts and Behaviors

Antidepressants increased the risk of suicidal thoughts and behavior in pediatric and young adults in short-term studies. Closely monitor all antidepressant-treated patients for clinical worsening, and for emergence of suicidal thoughts and behaviors [see Warnings and Precautions (5.2)].

1 INDICATIONS AND USAGE

LATUDA is indicated for:

- Treatment of adult and adolescent patients (13 to 17 years) with schizophrenia [see Clinical Studies (14.1)].
- Monotherapy treatment of adult and pediatric patients (10 to 17 years) with major depressive episode associated with bipolar I disorder (bipolar depression) [see Clinical Studies (14.2)].
- Adjunctive treatment with lithium or valproate in adult patients with major depressive episode associated with bipolar I disorder (bipolar depression) [see Clinical Studies (14.2)].

2 DOSAGE AND ADMINISTRATION

2.1 Schizophrenia

Adults

The recommended starting dose of LATUDA is 40 mg once daily. Initial dose titration is not required. LATUDA has been shown to be effective in a dose range of 40 mg per day to 160 mg per day [see Clinical Studies (14.1)]. The maximum recommended dose is 160 mg per day.

Adolescents (13 – 17 years)

The recommended starting dose of LATUDA is 40 mg once daily. Initial dose titration is not required. LATUDA has been shown to be effective in a dose range of 40 mg per day to 80 mg per day [see Clinical Studies (14.1)]. The maximum recommended dose is 80 mg per day.

2.2 Depressive Episodes Associated with Bipolar I Disorder

Adults

The recommended starting dose of LATUDA is 20 mg given once daily as monotherapy or as adjunctive therapy with lithium or valproate. Initial dose titration is not required. LATUDA has been shown to be effective in a dose range of 20 mg per day to 120 mg per day as monotherapy or as adjunctive therapy with lithium or valproate [see Clinical Studies (14.2)]. The maximum recommended dose, as monotherapy or as adjunctive therapy with lithium or valproate, is 120 mg per day. In the monotherapy study, the higher dose range (80 mg to 120 mg per day) did not provide additional efficacy, on average, compared to the lower dose range (20 to 60 mg per day) [see Clinical Studies (14.2)].

Pediatric Patients (10 – 17 years)

The recommended starting dose of LATUDA is 20 mg given once daily as monotherapy. Initial dose titration is not required. The dose may be increased after one week based on clinical response. LATUDA has been shown to be effective in a dose range of 20 mg per day to 80 mg per day as monotherapy. At the end of the clinical study, most of the patients (67%) received 20 mg or 40 mg once daily [see Clinical Studies (14.2)]. The maximum recommended dose is 80 mg per day.

The efficacy of LATUDA in the treatment of mania associated with bipolar disorder has not been established.

2.3 Administration Information

LATUDA should be taken with food (at least 350 calories). Administration with food substantially increases the absorption of LATUDA. Administration with food increases the AUC approximately 2-fold and increases the Cmax approximately 3-fold. In the clinical studies, LATUDA was administered with food [see Clinical Pharmacology (12.3)].

The effectiveness of LATUDA for longer-term use, that is, for more than 6 weeks, has not been established in controlled studies. Therefore, the physician who elects to use LATUDA for extended periods should periodically re-evaluate the long-term usefulness of the drug for the individual patient [see Dosage and Administration (2.1and 2.2)].

2.4 Dose Modifications for Renal Impairment

Dose adjustment is recommended in moderate (creatinine clearance: 30 to <50 mL/min) and severe renal impairment (creatinine clearance <30 mL/min) patients. The recommended starting dose is 20 mg per day. The dose in these patients should not exceed 80 mg per day [see Use in Specific Populations (8.6)].

2.5 Dose Modifications for Hepatic Impairment

Dose adjustment is recommended in moderate (Child-Pugh Score = 7 to 9) and severe hepatic impairment (Child-Pugh Score = 10 to 15) patients. The recommended starting dose is 20 mg per day. The dose in moderate hepatic impairment patients should not exceed 80 mg per day and the dose in severe hepatic impairment patients should not exceed 40 per mg/day [see Use in Specific Populations (8.7)].

2.6 Dose Modifications Due to Drug Interactions of CYP3A4 Inhibitors and CYP3A4 Inducers

Concomitant Use with CYP3A4 Inhibitors

LATUDA should not be used concomitantly with a strong CYP3A4 inhibitor (e.g., ketoconazole, clarithromycin, ritonavir, voriconazole, mibefradil, etc.) [see Contraindications (4)].

If LATUDA is being prescribed and a moderate CYP3A4 inhibitor (e.g. diltiazem, atazanavir, erythromycin, fluconazole, verapamil etc.) is added to the therapy, the LATUDA dose should be reduced to half of the original dose level. Similarly, if a moderate CYP3A4 inhibitor is being prescribed and LATUDA is added to the therapy, the recommended starting dose of LATUDA is 20 mg per day, and the maximum recommended dose of LATUDA is 80 mg per day [see Contraindications (4), Drug Interactions (7.1)].

Grapefruit and grapefruit juice should be avoided in patients taking LATUDA, since these may inhibit CYP3A4 and alter LATUDA concentrations [see Drug Interactions (7.1)].

Concomitant Use with CYP3A4 Inducers

LATUDA should not be used concomitantly with a strong CYP3A4 inducer (e.g., rifampin, avasimibe, St. John's wort, phenytoin, carbamazepine, etc.) [see Contraindications (4); Drug Interactions (7.1)]. If LATUDA is used concomitantly with a moderate CYP3A4 inducer, it may be necessary to increase the LATUDA dose after chronic treatment (7 days or more) with the CYP3A4 inducer.

3 DOSAGE FORMS AND STRENGTHS

LATUDA tablets are available in the following shape and color (Table 1) with respective one-sided debossing.

Table 1: LATUDA Tablet Presentations
Tablet Strength | Tablet Color/Shape | Tablet Markings
20 mg | white to off-white round | L20
40 mg | white to off-white round | L40
60 mg | white to off-white oblong | L60
80 mg | pale green oval | L80
120 mg | white to off-white oval | L120

4 CONTRAINDICATIONS

- Known hypersensitivity to lurasidone HCl or any components in the formulation. Angioedema has been observed with lurasidone [see Adverse Reactions (6.1)].
- Strong CYP3A4 inhibitors (e.g., ketoconazole, clarithromycin, ritonavir, voriconazole, mibefradil, etc.) [see Drug Interactions (7.1)].
- Strong CYP3A4 inducers (e.g., rifampin, avasimibe, St. John's wort, phenytoin, carbamazepine, etc.) [see Drug Interactions (7.1)].

5 WARNINGS AND PRECAUTIONS

5.1 Increased Mortality in Elderly Patients with Dementia-Related Psychosis

Elderly patients with dementia-related psychosis treated with antipsychotic drugs are at an increased risk of death. Analyses of 17 placebo-controlled trials (modal duration of 10 weeks), largely in patients taking atypical antipsychotic drugs, revealed a risk of death in drug-treated patients of between 1.6- to 1.7-times the risk of death in placebo-treated patients. Over the course of a typical 10-week controlled trial, the rate of death in drug-treated patients was about 4.5%, compared to a rate of about 2.6% in the placebo group. Although the causes of death were varied, most of the deaths appeared to be either cardiovascular (e.g., heart failure, sudden death) or infectious (e.g., pneumonia) in nature. LATUDA is not approved for the treatment of patients with dementia-related psychosis [see Boxed Warning, Warnings and Precautions (5.3)].

5.2 Suicidal Thoughts and Behaviors in Pediatric and Young Adult Patients

In pooled analyses of placebo-controlled trials of antidepressant drugs (SSRIs and other antidepressant classes) that included approximately 77,000 adult patients, and over 4,400 pediatric patients, the incidence of suicidal thoughts and behaviors in pediatric and young adult patients was greater in antidepressant-treated patients than in placebo-treated patients. The drug-placebo differences in the number of cases of suicidal thoughts and behaviors per 1000 patients treated are provided in Table 2.

No suicides occurred in any of the pediatric studies. There were suicides in the adult studies, but the number was not sufficient to reach any conclusion about antidepressant drug effect on suicide.

Table 2: Risk Differences of the Number of Cases of Suicidal Thoughts or Behaviors in the Pooled Placebo-Controlled Trials of Antidepressants in Pediatric and Adult Patients
Age Range | Drug-Placebo Difference in Number of Patients of Suicidal Thoughts or Behaviors per 1000 Patients Treated
 | Increases Compared to Placebo
<18 | 14 additional patients
18-24 | 5 additional patients
 | Decreases Compared to Placebo
25-64 | 1 fewer patient
≥65 | 6 fewer patients

It is unknown whether the risk of suicidal thoughts and behaviors in pediatric and young adult patients extends to longer-term use, i.e., beyond four months. However, there is substantial evidence from placebo-controlled maintenance studies in adults with MDD that antidepressants delay the recurrence of depression.

Monitor all antidepressant-treated patients for clinical worsening and emergence of suicidal thoughts and behaviors, especially during the initial few months of drug therapy and at times of dosage changes. Counsel family members or caregivers of patients to monitor for changes in behavior and to alert the healthcare provider. Consider changing the therapeutic regimen, including possibly discontinuing LATUDA, in patients whose depression is persistently worse, or who are experiencing emergent suicidal thoughts or behaviors.

5.3 Cerebrovascular Adverse Reactions, Including Stroke in Elderly Patients with Dementia-Related Psychosis

In placebo-controlled trials with risperidone, aripiprazole, and olanzapine in elderly subjects with dementia, there was a higher incidence of cerebrovascular adverse reactions (cerebrovascular accidents and transient ischemic attacks), including fatalities, compared to placebo-treated subjects. LATUDA is not approved for the treatment of patients with dementia-related psychosis [see Boxed Warning, Warnings and Precautions (5.1)].

5.4 Neuroleptic Malignant Syndrome

A potentially fatal symptom complex sometimes referred to as Neuroleptic Malignant Syndrome (NMS) has been reported in association with administration of antipsychotic drugs, including LATUDA. Clinical manifestations of NMS are hyperpyrexia, muscle rigidity, altered mental status, and evidence of autonomic instability. Additional signs may include elevated creatine phosphokinase, myoglobinuria (rhabdomyolysis), and acute renal failure.

If NMS is suspected, immediately discontinue LATUDA and provide intensive symptomatic treatment and monitoring.

5.5 Tardive Dyskinesia

Tardive dyskinesia is a syndrome consisting of potentially irreversible, involuntary, dyskinetic movements that can develop in patients treated with antipsychotic drugs. Although the prevalence of the syndrome appears to be highest among the elderly, especially elderly women, it is impossible to rely upon prevalence estimates to predict, at the inception of antipsychotic treatment, which patients are likely to develop the syndrome. Whether antipsychotic drug products differ in their potential to cause tardive dyskinesia is unknown.

The risk of developing tardive dyskinesia and the likelihood that it will become irreversible are believed to increase as the duration of treatment and the total cumulative dose of antipsychotic drugs administered to the patient increase. However, the syndrome can develop, although much less commonly, after relatively brief treatment periods at low doses or may even arise after discontinuation of treatment.

The syndrome may remit, partially or completely, if antipsychotic treatment is withdrawn. Antipsychotic treatment, itself, however, may suppress (or partially suppress) the signs and symptoms of the syndrome and thereby may possibly mask the underlying process. The effect that symptomatic suppression has upon the long-term course of the syndrome is unknown.

Given these considerations, LATUDA should be prescribed in a manner that is most likely to minimize the occurrence of tardive dyskinesia. Chronic antipsychotic treatment should generally be reserved for patients who suffer from a chronic illness that (1) is known to respond to antipsychotic drugs, and (2) for whom alternative, equally effective, but potentially less harmful treatments are not available or appropriate. In patients who do require chronic treatment, the smallest dose and the shortest duration of treatment producing a satisfactory clinical response should be sought. The need for continued treatment should be reassessed periodically.

If signs and symptoms of tardive dyskinesia appear in a patient on LATUDA, drug discontinuation should be considered. However, some patients may require treatment with LATUDA despite the presence of the syndrome.

5.6 Metabolic Changes

Atypical antipsychotic drugs have been associated with metabolic changes that may increase cardiovascular/cerebrovascular risk. These metabolic changes include hyperglycemia, dyslipidemia, and body weight gain. While all of the drugs in the class have been shown to produce some metabolic changes, each drug has its own specific risk profile.

Hyperglycemia and Diabetes Mellitus

Hyperglycemia, in some cases extreme and associated with ketoacidosis or hyperosmolar coma or death, has been reported in patients treated with atypical antipsychotics. Assessment of the relationship between atypical antipsychotic use and glucose abnormalities is complicated by the possibility of an increased background risk of diabetes mellitus in patients with schizophrenia and the increasing incidence of diabetes mellitus in the general population. Given these confounders, the relationship between atypical antipsychotic use and hyperglycemia-related adverse events is not completely understood. However, epidemiological studies suggest an increased risk of hyperglycemia-related adverse events in patients treated with the atypical antipsychotics.

Patients with an established diagnosis of diabetes mellitus who are started on atypical antipsychotics should be monitored regularly for worsening of glucose control. Patients with risk factors for diabetes mellitus (e.g., obesity, family history of diabetes) who are starting treatment with atypical antipsychotics should undergo fasting blood glucose testing at the beginning of treatment and periodically during treatment. Any patient treated with atypical antipsychotics should be monitored for symptoms of hyperglycemia including polydipsia, polyuria, polyphagia, and weakness. Patients who develop symptoms of hyperglycemia during treatment with atypical antipsychotics should undergo fasting blood glucose testing. In some cases, hyperglycemia has resolved when the atypical antipsychotic was discontinued; however, some patients required continuation of anti-diabetic treatment despite discontinuation of the suspect drug.

Schizophrenia

Adults

Pooled data from short-term, placebo-controlled schizophrenia studies are presented in Table 3.

Table 3: Change in Fasting Glucose in Adult Schizophrenia Studies
 |  |  | LATUDA
 | Placebo | 20 mg/day | 40 mg/day | 80 mg/day | 120 mg/day | 160 mg/day
Mean Change from Baseline (mg/dL)
 | n=680 | n=71 | n=478 | n=508 | n=283 | n=113
Serum Glucose | -0.0 | -0.6 | +2.6 | -0.4 | +2.5 | +2.5
Proportion of Patients with Shifts to ≥ 126 mg/dL
Serum Glucose (≥ 126 mg/dL) | 8.3% (52/628) | 11.7% (7/60) | 12.7% (57/449) | 6.8% (32/472) | 10.0% (26/260) | 5.6% (6/108)

In the uncontrolled, longer-term schizophrenia studies (primarily open-label extension studies), LATUDA was associated with a mean change in glucose of +1.8 mg/dL at week 24 (n=355), +0.8 mg/dL at week 36 (n=299) and +2.3 mg/dL at week 52 (n=307).

Adolescents

In studies of adolescents and adults with schizophrenia, changes in fasting glucose were similar. In the short-term, placebo-controlled study of adolescents, fasting serum glucose mean values were -1.3 mg/dL for placebo (n=95), +0.1 mg/dL for 40 mg/day (n=90), and +1.8 mg/dL for 80 mg/day (n=92).

Bipolar Depression

Adults

Monotherapy

Data from the adult short-term, flexible-dose, placebo-controlled monotherapy bipolar depression study are presented in Table 4.

Table 4: Change in Fasting Glucose in the Adult Monotherapy Bipolar Depression Study
 |  | LATUDA
 | Placebo | 20 to 60 mg/day | 80 to 120 mg/day
Mean Change from Baseline (mg/dL)
 | n=148 | n=140 | n=143
Serum Glucose | +1.8 | -0.8 | +1.8
Proportion of Patients with Shifts to ≥ 126 mg/dL
Serum Glucose (≥ 126 mg/dL) | 4.3% (6/141) | 2.2% (3/138) | 6.4% (9/141)
Patients were randomized to flexibly dosed LATUDA 20 to 60 mg/day, LATUDA 80 to 120 mg/day, or placebo

In the uncontrolled, open-label, longer-term bipolar depression study, patients who received LATUDA as monotherapy in the short-term study and continued in the longer-term study, had a mean change in glucose of +1.2 mg/dL at week 24 (n=129).

Adjunctive Therapy with Lithium or Valproate

Data from the adult short-term, flexible-dosed, placebo-controlled adjunctive therapy bipolar depression studies are presented in Table 5.

Table 5: Change in Fasting Glucose in the Adult Adjunctive Therapy Bipolar Depression Studies
 |  | LATUDA
 | Placebo | 20 to 120 mg/day
Mean Change from Baseline (mg/dL)
 | n=302 | n=319
Serum Glucose | -0.9 | +1.2
Proportion of Patients with Shifts to ≥ 126 mg/dL
Serum Glucose (≥ 126 mg/dL) | 1.0% (3/290) | 1.3% (4/316)
Patients were randomized to flexibly dosed LATUDA 20 to 120 mg/day or placebo as adjunctive therapy with lithium or valproate.

In the uncontrolled, open-label, longer-term bipolar depression study, patients who received LATUDA as adjunctive therapy with either lithium or valproate in the short-term study and continued in the longer-term study, had a mean change in glucose of +1.7 mg/dL at week 24 (n=88).

Pediatric Patients (10 to 17 years)

In studies of pediatric patients 10 to 17 years and adults with bipolar depression, changes in fasting glucose were similar. In the 6-week, placebo-controlled study of pediatric patients with bipolar depression, mean change in fasting glucose was +1.6 mg/dL for LATUDA 20 to 80 mg/day (n=145) and -0.5 mg/dL for placebo (n=145).

Pediatric Patients (6 to 17 years)

In a 104-week, open-label study in pediatric patients with schizophrenia, bipolar depression, or autistic disorder, 7% of patients with a normal baseline fasting glucose experienced a shift to high at endpoint while taking lurasidone.

Dyslipidemia

Undesirable alterations in lipids have been observed in patients treated with atypical antipsychotics.

Schizophrenia

Adults

Pooled data from short-term, placebo-controlled schizophrenia studies are presented in Table 6.

Table 6: Change in Fasting Lipids in Adult Schizophrenia Studies
 |  |  | LATUDA
 | Placebo | 20 mg/day | 40 mg/day | 80 mg/day | 120 mg/day | 160 mg/day
Mean Change from Baseline (mg/dL)
 | n=660 | n=71 | n=466 | n=499 | n=268 | n=115
Total Cholesterol | -5.8 | -12.3 | -5.7 | -6.2 | -3.8 | -6.9
Triglycerides | -13.4 | -29.1 | -5.1 | -13.0 | -3.1 | -10.6
Proportion of Patients with Shifts
Total Cholesterol (≥ 240 mg/dL) | 5.3% (30/571) | 13.8% (8/58) | 6.2% (25/402) | 5.3% (23/434) | 3.8% (9/238) | 4.0% (4/101)
Triglycerides (≥ 200 mg/dL) | 10.1% (53/526) | 14.3% (7/49) | 10.8% (41/379) | 6.3% (25/400) | 10.5% (22/209) | 7.0% (7/100)

In the uncontrolled, longer-term schizophrenia studies (primarily open-label extension studies), LATUDA was associated with a mean change in total cholesterol and triglycerides of -3.8 (n=356) and -15.1 (n=357) mg/dL at week 24, -3.1 (n=303) and -4.8 (n=303) mg/dL at week 36 and -2.5 (n=307) and -6.9 (n=307) mg/dL at week 52, respectively.

Adolescents

In the adolescent short-term, placebo-controlled study, fasting serum cholesterol mean values were -9.6 mg/dL for placebo (n=95), -4.4 mg/dL for 40 mg/day (n=89), and +1.6 mg/dL for 80 mg/day (n=92), and fasting serum triglyceride mean values were +0.1 mg/dL for placebo (n=95), -0.6 mg/dL for 40 mg/day (n=89), and +8.5 mg/dL for 80 mg/day (n=92).

Bipolar Depression

Adults

Monotherapy

Data from the adult short-term, flexible-dosed, placebo-controlled, monotherapy bipolar depression study are presented in Table 7.

Table 7: Change in Fasting Lipids in the Adult Monotherapy Bipolar Depression Study
 |  | LATUDA
 | Placebo | 20 to 60 mg/day | 80 to 120 mg/day
Mean Change from Baseline (mg/dL)
 | n=147 | n=140 |  | n=144
Total cholesterol | -3.2 | +1.2 |  | -4.6
Triglycerides | +6.0 | +5.6 |  | +0.4
Proportion of Patients with Shifts
Total cholesterol (≥ 240 mg/dL) | 4.2% (5/118) | 4.4% (5/113) |  | 4.4% (5/114)
Triglycerides (≥ 200 mg/dL) | 4.8% (6/126) | 10.1% (12/119) |  | 9.8% (12/122)
Patients were randomized to flexibly dosed LATUDA 20 to 60 mg/day, LATUDA 80 to 120 mg/day, or placebo

In the uncontrolled, open-label, longer-term bipolar depression study, patients who received LATUDA as monotherapy in the short-term and continued in the longer-term study had a mean change in total cholesterol and triglycerides of -0.5 mg/dL (n=130) and -1.0 mg/dL (n=130) at week 24, respectively.

Adjunctive Therapy with Lithium or Valproate

Data from the adult short-term, flexible-dosed, placebo-controlled, adjunctive therapy bipolar depression studies are presented in Table 8.

Table 8: Change in Fasting Lipids in the Adult Adjunctive Therapy Bipolar Depression Studies
 |  | LATUDA
 | Placebo | 20 to 120 mg/day
Mean Change from Baseline (mg/dL)
 | n=303 | n=321
Total cholesterol | -2.9 | -3.1
Triglycerides | -4.6 | +4.6
Proportion of Patients with Shifts
Total cholesterol (≥ 240 mg/dL) | 5.7% (15/263) | 5.4% (15/276)
Triglycerides (≥ 200 mg/dL) | 8.6% (21/243) | 10.8% (28/260)
Patients were randomized to flexibly dosed LATUDA 20 to 120 mg/day or placebo as adjunctive therapy with lithium or valproate.

In the uncontrolled, open-label, longer-term bipolar depression study, patients who received LATUDA as adjunctive therapy with either lithium or valproate in the short-term study and continued in the longer-term study, had a mean change in total cholesterol and triglycerides of
-0.9 (n=88) and +5.3 (n=88) mg/dL at week 24, respectively.

Pediatric Patients (10 to 17 years)

In the 6-week, placebo-controlled bipolar depression study with pediatric patients 10 to 17 years, mean change in fasting cholesterol was -6.3 mg/dL for LATUDA 20 to 80 mg/day (n=144) and
-1.4 mg/dL for placebo (n=145), and mean change in fasting triglyceride was -7.6 mg/dL for LATUDA 20 to 80 mg/day (n=144) and +5.9 mg/dL for placebo (n=145).

Pediatric Patients (6 to 17 years)

In a 104-week, open-label study of pediatric patients with schizophrenia, bipolar depression, or autistic disorder, shifts in baseline fasting cholesterol from normal to high at endpoint were reported in 12% (total cholesterol), 3% (LDL cholesterol), and shifts in baseline from normal to low were reported in 27% (HDL cholesterol) of patients taking lurasidone. Of patients with normal baseline fasting triglycerides, 12% experienced shifts to high.

Weight Gain

Weight gain has been observed with atypical antipsychotic use. Clinical monitoring of weight is recommended.

Schizophrenia

Adults

Pooled data from short-term, placebo-controlled schizophrenia studies are presented in Table 9. The mean weight gain was +0.43 kg for LATUDA-treated patients compared to -0.02 kg for placebo-treated patients. Change in weight from baseline for olanzapine was +4.15 kg and for quetiapine extended-release was +2.09 kg in Studies 3 and 5 [see Clinical Studies (14.1)], respectively. The proportion of patients with a ≥7% increase in body weight (at Endpoint) was 4.8% for LATUDA-treated patients and 3.3% for placebo-treated patients.

Table 9: Mean Change in Weight (kg) from Baseline in Adult Schizophrenia Studies
 |  |  | LATUDA
 | Placebo (n=696) | 20 mg/day (n=71) | 40 mg/day (n=484) | 80 mg/day (n=526) | 120 mg/day (n=291) | 160 mg/day (n=114)
All Patients | -0.02 | -0.15 | +0.22 | +0.54 | +0.68 | +0.60

In the uncontrolled, longer-term schizophrenia studies (primarily open-label extension studies), LATUDA was associated with a mean change in weight of -0.69 kg at week 24 (n=755), -0.59 kg at week 36 (n=443) and -0.73 kg at week 52 (n=377).

Adolescents

Data from the short-term, placebo-controlled adolescent schizophrenia study are presented in Table 10. The mean change in weight gain was +0.5 kg for LATUDA-treated patients compared to +0.2 kg for placebo-treated patients. The proportion of patients with a ≥7% increase in body weight (at Endpoint) was 3.3% for LATUDA-treated patients and 4.5% for placebo-treated patients.

Table 10: Mean Change in Weight (kg) from Baseline in the Adolescent Schizophrenia Study
 | Placebo (n=111) | LATUDA
 | Placebo (n=111) | 40 mg/day (n=109) | 80 mg/day (n=104)
All Patients | +0.2 | +0.3 | +0.7

Bipolar Depression

Adults

Monotherapy

Data from the adult short-term, flexible-dosed, placebo-controlled monotherapy bipolar depression study are presented in Table 11. The mean change in weight gain was +0.29 kg for LATUDA-treated patients compared to -0.04 kg for placebo-treated patients. The proportion of patients with a ≥7% increase in body weight (at Endpoint) was 2.4% for LATUDA-treated patients and 0.7% for placebo-treated patients.

Table 11: Mean Change in Weight (kg) from Baseline in the Adult Monotherapy Bipolar Depression Study
 |  | LATUDA
 | Placebo (n=151) | 20 to 60 mg/day (n=143) | 80 to 120 mg/day (n=147)
All Patients | -0.04 | +0.56 |  | +0.02
Patients were randomized to flexibly dosed LATUDA 20 to 60 mg/day, LATUDA 80 to 120 mg/day, or placebo

In the uncontrolled, open-label, longer-term bipolar depression study, patients who received LATUDA as monotherapy in the short-term and continued in the longer-term study had a mean change in weight of -0.02 kg at week 24 (n=130).

Adjunctive Therapy with Lithium or Valproate

Data from the adult short-term, flexible-dosed, placebo-controlled adjunctive therapy bipolar depression studies are presented in Table 12. The mean change in weight gain was +0.11 kg for LATUDA-treated patients compared to +0.16 kg for placebo-treated patients. The proportion of patients with a ≥7% increase in body weight (at Endpoint) was 3.1% for LATUDA-treated patients and 0.3% for placebo-treated patients.

Table 12: Mean Change in Weight (kg) from Baseline in the Adult Adjunctive Therapy Bipolar Depression Studies
 |  | LATUDA
 | Placebo (n=307) | 20 to 120 mg/day (n=327)
All Patients | +0.16 | +0.11
Patients were randomized to flexibly dosed LATUDA 20 to 120 mg/day or placebo as adjunctive therapy with lithium or valproate.

In the uncontrolled, open-label, longer-term bipolar depression study, patients who were treated with LATUDA, as adjunctive therapy with either lithium or valproate in the short-term and continued in the longer-term study, had a mean change in weight of +1.28 kg at week 24 (n=86).

Pediatric Patients (10 to 17 years)

Data from the 6-week, placebo-controlled bipolar depression study in patients 10 to 17 years are presented in Table 13. The mean change in weight gain was +0.7 kg for LATUDA-treated patients compared to +0.5 kg for placebo-treated patients. The proportion of patients with a ≥7% increase in body weight (at Endpoint) was 4.0% for LATUDA-treated patients and 5.3% for placebo-treated patients.

Table 13: Mean Change in Weight (kg) from Baseline in the Bipolar Depression Study in Pediatric Patients (10 to 17 years)
 |  | LATUDA
 | Placebo (n=170) | 20 to 80 mg/day (n=175)
All Patients | +0.5 | +0.7

Pediatric Patients (6 to 17 years)

In a long-term, open-label study that enrolled pediatric patients with schizophrenia, bipolar depression, or autistic disorder from three short-term, placebo-controlled trials, 54% (378/701) received lurasidone for 104 weeks. The mean increase in weight from open-label baseline to Week 104 was 5.85 kg. To adjust for normal growth, z-scores were derived (measured in standard deviations [SD]), which normalize for the natural growth of children and adolescents by comparisons to age- and sex-matched population standards. A z-score change <0.5 SD is considered not clinically significant. In this trial, the mean change in z-score from open-label baseline to Week 104 was -0.06 SD for body weight and -0.13 SD for body mass index (BMI), indicating minimal deviation from the normal curve for weight gain.

5.7 Hyperprolactinemia

As with other drugs that antagonize dopamine D2 receptors, LATUDA elevates prolactin levels.

Hyperprolactinemia may suppress hypothalamic GnRH, resulting in reduced pituitary gonadotrophin secretion. This, in turn, may inhibit reproductive function by impairing gonadal steroidogenesis in both female and male patients. Galactorrhea, amenorrhea, gynecomastia, and impotence have been reported with prolactin-elevating compounds. Long-standing hyperprolactinemia, when associated with hypogonadism, may lead to decreased bone density in both female and male patients [see Adverse Reactions (6)].

Tissue culture experiments indicate that approximately one-third of human breast cancers are prolactin-dependent in vitro, a factor of potential importance if the prescription of these drugs is considered in a patient with previously detected breast cancer. As is common with compounds which increase prolactin release, an increase in mammary gland neoplasia was observed in a carcinogenicity study conducted with lurasidone in rats and mice [see Nonclinical Toxicology (13)]. Published epidemiologic studies have shown inconsistent results when exploring the potential association between hyperprolactinemia and breast cancer.

Schizophrenia

Adults

In short-term, placebo-controlled schizophrenia studies, the median change from baseline to endpoint in prolactin levels for LATUDA-treated patients was +0.4 ng/mL and was -1.9 ng/mL in the placebo-treated patients. The median change from baseline to endpoint for males was +0.5 ng/mL and for females was -0.2 ng/mL. Median changes for prolactin by dose are shown in Table 14.

Table 14: Median Change in Prolactin (ng/mL) from Baseline in Adult Schizophrenia Studies
 |  |  | LATUDA
 | Placebo | 20 mg/day | 40 mg/day | 80 mg/day | 120 mg/day | 160 mg/day
All Patients | -1.9 (n=672) | -1.1 (n=70) | -1.4 (n=476) | -0.2 (n=495) | +3.3 (n=284) | +3.3 (n=115)
Females | -5.1 (n=200) | -0.7 (n=19) | -4.0 (n=149) | -0.2 (n=150) | +6.7 (n=70) | +7.1 (n=36)
Males | -1.3 (n=472) | -1.2 (n=51) | -0.7 (n=327) | -0.2 (n=345) | +3.1 (n=214) | +2.4 (n=79)

The proportion of patients with prolactin elevations ≥5× upper limit of normal (ULN) was 2.8% for LATUDA-treated patients and = 1.0% for placebo-treated patients. The proportion of female patients with prolactin elevations ≥5x ULN was 5.7% for LATUDA-treated patients and = 2.0% for placebo-treated female patients. The proportion of male patients with prolactin elevations ≥5x ULN was 1.6% and 0.6% for placebo-treated male patients.

In the uncontrolled longer-term schizophrenia studies (primarily open-label extension studies), LATUDA was associated with a median change in prolactin of -0.9 ng/mL at week 24 (n=357),
-5.3 ng/mL at week 36 (n=190) and -2.2 ng/mL at week 52 (n=307).

Adolescents

In the short-term, placebo-controlled adolescent schizophrenia study, the median change from baseline to endpoint in prolactin levels for LATUDA-treated patients was +1.1 ng/mL and was +0.1 ng/mL for placebo-treated patients. For LATUDA-treated patients, the median change from baseline to endpoint for males was +1.0 ng/mL and for females was +2.6 ng/mL. Median changes for prolactin by dose are shown in Table 15.

Table 15: Median Change in Prolactin (ng/mL) from Baseline in the Adolescent Schizophrenia Study
 | Placebo | LATUDA 40 mg/day | LATUDA 80 mg/day
All Patients | +0.10 (n=103) | +0.75 (n=102) | +1.20 (n=99)
Females | +0.70 (n=39) | +0.60 (n=42) | +4.40 (n=33)
Males | 0.00 (n=64) | +0.75 (n=60) | +1.00 (n=66)

The proportion of patients with prolactin elevations ≥5x ULN was 0.5% for LATUDA-treated patients and 1.0% for placebo-treated patients. The proportion of female patients with prolactin elevations ≥5x ULN was 1.3% for LATUDA-treated patients and 0% for placebo-treated female patients. The proportion of male patients with prolactin elevations ≥5x ULN was 0% for LATUDA treated patients and 1.6% for placebo-treated male patients.

Bipolar Depression

Adults

Monotherapy

The median change from baseline to endpoint in prolactin levels, in the adult short-term, flexible-dosed, placebo-controlled monotherapy bipolar depression study, was +1.7 ng/mL and +3.5 ng/mL with LATUDA 20 to 60 mg/day and 80 to 120 mg/day, respectively compared to +0.3 ng/mL with placebo-treated patients. The median change from baseline to endpoint for males was +1.5 ng/mL and for females was +3.1 ng/mL. Median changes for prolactin by dose range are shown in Table 16.

Table 16: Median Change in Prolactin (ng/mL) from Baseline in the Adult Monotherapy Bipolar Depression Study
 |  | LATUDA
 | Placebo | 20 to 60 mg/day | 80 to 120 mg/day
All Patients | +0.3 (n=147) | +1.7 (n=140) |  | +3.5 (n=144)
Females | 0.0 (n=82) | +1.8 (n=78) |  | +5.3 (n=88)
Males | +0.4 (n=65) | +1.2 (n=62) |  | +1.9 (n=56)
Patients were randomized to flexibly dosed LATUDA 20 to 60 mg/day, LATUDA 80 to 120 mg/day, or placebo

The proportion of patients with prolactin elevations ≥5x upper limit of normal (ULN) was 0.4% for LATUDA-treated patients and 0.0% for placebo-treated patients. The proportion of female patients with prolactin elevations ≥5x ULN was 0.6% for LATUDA-treated patients and 0% for placebo-treated female patients. The proportion of male patients with prolactin elevations ≥5x ULN was 0% and 0% for placebo-treated male patients.

In the uncontrolled, open-label, longer-term bipolar depression study, patients who were treated with LATUDA as monotherapy in the short-term and continued in the longer-term study, had a median change in prolactin of -1.15 ng/mL at week 24 (n=130).

Adjunctive Therapy with Lithium or Valproate

The median change from baseline to endpoint in prolactin levels, in the adult short-term, flexible-dosed, placebo-controlled adjunctive therapy bipolar depression studies was +2.8 ng/mL with LATUDA 20 to 120 mg/day compared to 0.0 ng/mL with placebo-treated patients. The median change from baseline to endpoint for males was +2.4 ng/mL and for females was +3.2 ng/mL. Median changes for prolactin across the dose range are shown in Table 17.

Table 17: Median Change in Prolactin (ng/mL) from Baseline in the Adult Adjunctive Therapy Bipolar Depression Studies
 |  | LATUDA
 | Placebo | 20 to 120 mg/day
All Patients | 0.0 (n=301) | +2.8 (n=321)
Females | +0.4 (n=156) | +3.2 (n=162)
Males | -0.1 (n=145) | +2.4 (n=159)
Patients were randomized to flexibly dosed LATUDA 20 to 120 mg/day or placebo as adjunctive therapy with lithium or valproate.

The proportion of patients with prolactin elevations ≥5x upper limit of normal (ULN) was 0.0% for LATUDA-treated patients and 0.0% for placebo-treated patients. The proportion of female patients with prolactin elevations ≥5x ULN was 0% for LATUDA-treated patients and 0% for placebo-treated female patients. The proportion of male patients with prolactin elevations ≥5x ULN was 0% and 0% for placebo-treated male patients.

In the uncontrolled, open-label, longer-term bipolar depression study, patients who were treated with LATUDA, as adjunctive therapy with either lithium or valproate, in the short-term and continued in the longer-term study, had a median change in prolactin of -2.9 ng/mL at week 24 (n=88).

Pediatric Patients (10 to 17 years)

In the 6-week, placebo-controlled bipolar depression study with pediatric patients 10 to 17 years, the median change from baseline to endpoint in prolactin levels for LATUDA-treated patients was +1.10 ng/mL and was +0.50 ng/mL for placebo-treated patients. For LATUDA-treated patients, the median change from baseline to endpoint for males was +0.85 ng/mL and for females was +2.50 ng/mL. Median changes for prolactin are shown in Table 18.

Table 18: Median Change in Prolactin (ng/mL) from Baseline in the Bipolar Depression Study in Pediatric Patients (10 to 17 years)
 |  | LATUDA
 | Placebo | 20 to 80 mg/day
All Patients | +0.50 (n=157) | +1.10 (n=165)
Females | +0.55 (n=78) | +2.50 (n=83)
Males | +0.50 (n=79) | +0.85 (n=82)

The proportion of patients with prolactin elevations ≥5x ULN was 0% for LATUDA-treated patients and 0.6% for placebo-treated patients. The proportion of female patients with prolactin elevations ≥5x ULN was 0% for LATUDA-treated patients and 1.3% for placebo-treated female patients. No male patients in the placebo or LATUDA treatment groups had prolactin elevations ≥5x ULN.

Pediatric Patients (6 to 17 years)

In a 104-week, open-label study of pediatric patients with schizophrenia, bipolar depression, or autistic disorder, the median changes from baseline to endpoint in serum prolactin levels were -0.20 ng/mL (all patients), -0.30 ng/mL (females), and -0.05 ng/mL (males). The proportions of patients with a markedly high prolactin level (≥5 times the upper limit of normal) at any time during open-label treatment were 2% (all patients), 3% (females), and 1% (males).

Adverse events among females in this trial that are potentially prolactin-related include galactorrhea (0.6%). Among male patients in this study, decreased libido was reported in one patient (0.2%) and there were no reports of impotence, gynecomastia, or galactorrhea.

5.8 Leukopenia, Neutropenia and Agranulocytosis

Leukopenia/neutropenia has been reported during treatment with antipsychotic agents. Agranulocytosis (including fatal cases) has been reported with other agents in the class.

Possible risk factors for leukopenia/neutropenia include pre-existing low white blood cell count (WBC) and history of drug-induced leukopenia/neutropenia. Patients with a pre-existing low WBC or a history of drug-induced leukopenia/neutropenia should have their complete blood count (CBC) monitored frequently during the first few months of therapy and LATUDA should be discontinued at the first sign of decline in WBC, in the absence of other causative factors.

Patients with neutropenia should be carefully monitored for fever or other symptoms or signs of infection and treated promptly if such symptoms or signs occur. Patients with severe neutropenia (absolute neutrophil count < 1000/mm^3) should discontinue LATUDA and have their WBC followed until recovery.

5.9 Orthostatic Hypotension and Syncope

LATUDA may cause orthostatic hypotension and syncope, perhaps due to its α1-adrenergic receptor antagonism. Associated adverse reactions can include dizziness, lightheadedness, tachycardia, and bradycardia. Generally, these risks are greatest at the beginning of treatment and during dose escalation. Patients at increased risk of these adverse reactions or at increased risk of developing complications from hypotension include those with dehydration, hypovolemia, treatment with antihypertensive medication, history of cardiovascular disease (e.g., heart failure, myocardial infarction, ischemia, or conduction abnormalities), history of cerebrovascular disease, as well as patients who are antipsychotic-naïve. In such patients, consider using a lower starting dose and slower titration, and monitor orthostatic vital signs.

Orthostatic hypotension, as assessed by vital sign measurement, was defined by the following vital sign changes: ≥ 20 mm Hg decrease in systolic blood pressure and ≥10 bpm increase in pulse from sitting to standing or supine to standing position.

Schizophrenia

Adults

The incidence of orthostatic hypotension and syncope reported as adverse events from short-term, placebo-controlled schizophrenia studies was (LATUDA incidence, placebo incidence): orthostatic hypotension [0.3% (5/1508), 0.1% (1/708)] and syncope [0.1% (2/1508), 0% (0/708)].

In short-term schizophrenia clinical studies, orthostatic hypotension, as assessed by vital signs, occurred with a frequency of 0.8% with LATUDA 40 mg, 2.1% with LATUDA 80 mg, 1.7% with LATUDA 120 mg and 0.8% with LATUDA 160 mg compared to 0.7% with placebo.

Adolescents

The incidence of orthostatic hypotension reported as adverse events from the short-term, placebo-controlled adolescent schizophrenia study was 0.5% (1/214) in LATUDA-treated patients and 0% (0/112) in placebo-treated patients. No syncope event was reported.

Orthostatic hypotension, as assessed by vital signs, occurred with a frequency of 0% with LATUDA 40 mg and 2.9% with LATUDA 80 mg, compared to 1.8% with placebo.

Bipolar Depression

Adults

Monotherapy

In the adult short-term, flexible-dose, placebo-controlled monotherapy bipolar depression study, there were no reported adverse events of orthostatic hypotension and syncope.

Orthostatic hypotension, as assessed by vital signs, occurred with a frequency of 0.6% with LATUDA 20 to 60 mg and 0.6% with LATUDA 80 to 120 mg compared to 0% with placebo.

Adjunctive Therapy with Lithium or Valproate

In the adult short-term, flexible-dose, placebo-controlled adjunctive therapy bipolar depression therapy studies, there were no reported adverse events of orthostatic hypotension and syncope. Orthostatic hypotension, as assessed by vital signs, occurred with a frequency of 1.1% with LATUDA 20 to 120 mg compared to 0.9% with placebo.

Pediatric Patients (10 to 17 years)

In the 6-week, placebo-controlled bipolar depression study in pediatric patients 10 to 17 years, there were no reported adverse events of orthostatic hypotension or syncope.

Orthostatic hypotension, as assessed by vital signs, occurred with a frequency of 1.1% with LATUDA 20 to 80 mg/day, compared to 0.6% with placebo.

5.10 Falls

LATUDA may cause somnolence, postural hypotension, motor and sensory instability, which may lead to falls and, consequently, fractures or other injuries. For patients with diseases, conditions, or medications that could exacerbate these effects, complete fall risk assessments when initiating antipsychotic treatment and recurrently for patients on long-term antipsychotic therapy.

5.11 Seizures

As with other antipsychotic drugs, LATUDA should be used cautiously in patients with a history of seizures or with conditions that lower the seizure threshold, e.g., Alzheimer's dementia. Conditions that lower the seizure threshold may be more prevalent in patients 65 years or older.

Schizophrenia

In adult short-term, placebo-controlled schizophrenia studies, seizures/convulsions occurred in 0.1% (2/1508) of patients treated with LATUDA compared to 0.1% (1/708) placebo-treated patients.

Bipolar Depression

Monotherapy

In the adult and pediatric 6-week, flexible-dose, placebo-controlled monotherapy bipolar depression studies, no patients experienced seizures/convulsions.

Adjunctive Therapy with Lithium or Valproate

In the adult short-term, flexible-dose, placebo-controlled adjunctive therapy bipolar depression studies, no patient experienced seizures/convulsions.

5.12 Potential for Cognitive and Motor Impairment

LATUDA, like other antipsychotics, has the potential to impair judgment, thinking or motor skills. Caution patients about operating hazardous machinery, including motor vehicles, until they are reasonably certain that therapy with LATUDA does not affect them adversely.

In clinical studies with LATUDA, somnolence included: hypersomnia, hypersomnolence, sedation and somnolence.

Schizophrenia

Adults

In short-term, placebo-controlled schizophrenia studies, somnolence was reported by 17.0% (256/1508) of patients treated with LATUDA (15.5% LATUDA 20 mg, 15.6% LATUDA 40 mg, 15.2% LATUDA 80 mg, 26.5% LATUDA 120 mg and 8.3% LATUDA 160 mg/day) compared to 7.1% (50/708) of placebo patients.

Adolescents

In the short-term, placebo-controlled adolescent schizophrenia study, somnolence was reported by 14.5% (31/214) of patients treated with LATUDA (15.5% LATUDA 40 mg and 13.5% LATUDA 80 mg,/day) compared to 7.1% (8/112) of placebo patients.

Bipolar Depression

Adults

Monotherapy

In the adult short-term, flexible-dosed, placebo-controlled monotherapy bipolar depression study, somnolence was reported by 7.3% (12/164) and 13.8% (23/167) with LATUDA 20 to 60 mg and 80 to 120 mg, respectively compared to 6.5% (11/168) of placebo patients.

Adjunctive Therapy with Lithium or Valproate

In the adult short-term, flexible-dosed, placebo-controlled adjunctive therapy bipolar depression studies, somnolence was reported by 11.4% (41/360) of patients treated with LATUDA 20-120 mg compared to 5.1% (17/334) of placebo patients.

Pediatric Patients (10 to 17 years)

In the 6-week, placebo-controlled bipolar depression study in pediatric patients 10 to 17 years, somnolence was reported by 11.4% (20/175) of patients treated with LATUDA 20 to 80 mg/day compared to 5.8% (10/172) of placebo treated patients.

5.13 Body Temperature Dysregulation

Disruption of the body's ability to reduce core body temperature has been attributed to antipsychotic agents. Appropriate care is advised when prescribing LATUDA for patients who will be experiencing conditions that may contribute to an elevation in core body temperature, e.g., exercising strenuously, exposure to extreme heat, receiving concomitant medication with anticholinergic activity, or being subject to dehydration.

5.14 Activation of Mania/Hypomania

Antidepressant treatment can increase the risk of developing a manic or hypomanic episode, particularly in patients with bipolar disorder. Monitor patients for the emergence of such episodes.

In the adult bipolar depression monotherapy and adjunctive therapy (with lithium or valproate) studies, less than 1% of subjects in the LATUDA and placebo groups developed manic or hypomanic episodes.

5.15 Dysphagia

Esophageal dysmotility and aspiration have been associated with antipsychotic drug use. Aspiration pneumonia is a common cause of morbidity and mortality in elderly patients, in particular those with advanced Alzheimer's dementia. LATUDA and other antipsychotic drugs should be used cautiously in patients at risk for aspiration pneumonia.

5.16 Neurological Adverse Reactions in Patients with Parkinson's Disease or Dementia with Lewy Bodies

Patients with Parkinson's Disease or Dementia with Lewy Bodies are reported to have an increased sensitivity to antipsychotic medication. Manifestations of this increased sensitivity include confusion, obtundation, postural instability with frequent falls, extrapyramidal symptoms, and clinical features consistent with the neuroleptic malignant syndrome.

6 ADVERSE REACTIONS

The following adverse reactions are discussed in more detail in other sections of the labeling:

- Increased Mortality in Elderly Patients with Dementia-Related Psychosis [see Boxed Warning and Warnings and Precautions (5.1)]
- Suicidal Thoughts and Behaviors [see Boxed Warning and Warnings and Precautions (5.2)]
- Cerebrovascular Adverse Reactions, Including Stroke, in Elderly Patients with Dementia-related Psychosis [see Warnings and Precautions (5.3)]
- Neuroleptic Malignant Syndrome [see Warnings and Precautions (5.4)]
- Tardive Dyskinesia [see Warnings and Precautions (5.5)]
- Metabolic Changes [see Warnings and Precautions (5.6)]
- Hyperprolactinemia [see Warnings and Precautions (5.7)]
- Leukopenia, Neutropenia, and Agranulocytosis [see Warnings and Precautions (5.8)]
- Orthostatic Hypotension and Syncope [see Warnings and Precautions (5.9)]
- Falls [see Warnings and Precautions (5.10)]
- Seizures [see Warnings and Precautions (5.11)]
- Potential for Cognitive and Motor Impairment [see Warnings and Precautions (5.12)]
- Body Temperature Dysregulation [see Warnings and Precautions (5.13)]
- Activation of Mania/Hypomania [see Warnings and Precautions (5.14)]
- Dysphagia [see Warnings and Precautions (5.15)]
- Neurological Adverse Reactions in Patients with Parkinson's Disease or Dementia with Lewy Bodies [see Warnings and Precautions (5.16)]

6.1 Clinical Trials Experience

Because clinical trials are conducted under widely varying conditions, adverse reaction rates observed in clinical trials of a drug cannot be directly compared to rates in the clinical trials of another drug and may not reflect the rates observed in clinical practice.

Adults

The information below is derived from an integrated clinical study database for LATUDA consisting of 3799 adult patients exposed to one or more doses of LATUDA for the treatment of schizophrenia, and bipolar depression in placebo-controlled studies. This experience corresponds with a total experience of 1250.9 patient-years. A total of 1106 LATUDA-treated patients had at least 24 weeks and 371 LATUDA-treated patients had at least 52 weeks of exposure.

Adverse events during exposure to study treatment were obtained by general inquiry and voluntarily reported adverse experiences, as well as results from physical examinations, vital signs, ECGs, weights and laboratory investigations. Adverse experiences were recorded by clinical investigators using their own terminology. In order to provide a meaningful estimate of the proportion of individuals experiencing adverse events, events were grouped in standardized categories using MedDRA terminology.

Schizophrenia

The following findings are based on the short-term, placebo-controlled premarketing adult studies for schizophrenia in which LATUDA was administered at daily doses ranging from 20 to 160 mg (n=1508).

Commonly Observed Adverse Reactions: The most common adverse reactions (incidence ≥ 5% and at least twice the rate of placebo) in patients treated with LATUDA were somnolence, akathisia, extrapyramidal symptoms, and nausea.

Adverse Reactions Associated with Discontinuation of Treatment: A total of 9.5% (143/1508) LATUDA-treated patients and 9.3% (66/708) of placebo-treated patients discontinued due to adverse reactions. There were no adverse reactions associated with discontinuation in subjects treated with LATUDA that were at least 2% and at least twice the placebo rate.

Adverse Reactions Occurring at an Incidence of 2% or More in LATUDA-Treated Patients: Adverse reactions associated with the use of LATUDA (incidence of 2% or greater, rounded to the nearest percent and LATUDA incidence greater than placebo) that occurred during acute therapy (up to 6 weeks in patients with schizophrenia) are shown in Table 19.

Table 19: Adverse Reactions in 2% or More of LATUDA-Treated Patients and That Occurred at Greater Incidence than in the Placebo-Treated Patients in Adult Short-term Schizophrenia Studies
 | Percentage of Patients Reporting Reaction
 | LATUDA
Body System or Organ Class | Placebo (N=708) (%) | 20 mg/day (N=71) (%) | 40 mg/day (N=487) (%) | 80 mg/day (N=538) (%) | 120 mg/day (N=291) (%) | 160 mg/day (N=121) (%) | All LATUDA (N=1508) (%)
Gastrointestinal Disorders
Nausea | 5 | 11 | 10 | 9 | 13 | 7 | 10
Vomiting | 6 | 7 | 6 | 9 | 9 | 7 | 8
Dyspepsia | 5 | 11 | 6 | 5 | 8 | 6 | 6
Salivary Hypersecretion | <1 | 1 | 1 | 2 | 4 | 2 | 2
Musculoskeletal and Connective Tissue Disorders
Back Pain | 2 | 0 | 4 | 3 | 4 | 0 | 3
Nervous System Disorders
Somnolence* | 7 | 15 | 16 | 15 | 26 | 8 | 17
Akathisia | 3 | 6 | 11 | 12 | 22 | 7 | 13
Extrapyramidal Disorder** | 6 | 6 | 11 | 12 | 22 | 13 | 14
Dizziness | 2 | 6 | 4 | 4 | 5 | 6 | 4
Psychiatric Disorders
Insomnia | 8 | 8 | 10 | 11 | 9 | 7 | 10
Agitation | 4 | 10 | 7 | 3 | 6 | 5 | 5
Anxiety | 4 | 3 | 6 | 4 | 7 | 3 | 5
Restlessness | 1 | 1 | 3 | 1 | 3 | 2 | 2
Note: Figures rounded to the nearest integer
* Somnolence includes adverse event terms: hypersomnia, hypersomnolence, sedation, and somnolence
** Extrapyramidal symptoms include adverse event terms: bradykinesia, cogwheel rigidity, drooling, dystonia, extrapyramidal disorder, hypokinesia, muscle rigidity, oculogyric crisis, oromandibular dystonia, parkinsonism, psychomotor retardation, tongue spasm, torticollis, tremor, and trismus

Dose-Related Adverse Reactions in the Schizophrenia Studies

Akathisia and extrapyramidal symptoms were dose-related. The frequency of akathisia increased with dose up to 120 mg/day (5.6% for LATUDA 20 mg, 10.7% for LATUDA 40 mg, 12.3% for LATUDA 80 mg, and 22.0% for LATUDA 120 mg). Akathisia was reported by 7.4% (9/121) of patients receiving 160 mg/day. Akathisia occurred in 3.0% of subjects receiving placebo. The frequency of extrapyramidal symptoms increased with dose up to 120 mg/day (5.6% for LATUDA 20 mg, 11.5% for LATUDA 40 mg, 11.9% for LATUDA 80 mg, and 22.0% for LATUDA 120 mg).

Bipolar Depression (Monotherapy)

The following findings are based on the adult short-term, placebo-controlled premarketing study for bipolar depression in which LATUDA was administered at daily doses ranging from 20 to 120 mg (n=331).

Commonly Observed Adverse Reactions: The most common adverse reactions (incidence ≥5%, in either dose group, and at least twice the rate of placebo) in patients treated with LATUDA were akathisia, extrapyramidal symptoms, somnolence, nausea, vomiting, diarrhea, and anxiety.

Adverse Reactions Associated with Discontinuation of Treatment: A total of 6.0% (20/331) LATUDA-treated patients and 5.4% (9/168) of placebo-treated patients discontinued due to adverse reactions. There were no adverse reactions associated with discontinuation in subjects treated with LATUDA that were at least 2% and at least twice the placebo rate.

Adverse Reactions Occurring at an Incidence of 2% or More in LATUDA-Treated Patients: Adverse reactions associated with the use of LATUDA (incidence of 2% or greater, rounded to the nearest percent and LATUDA incidence greater than placebo) that occurred during acute therapy (up to 6 weeks in patients with bipolar depression) are shown in Table 20.

Table 20: Adverse Reactions in 2% or More of LATUDA-Treated Patients and That Occurred at Greater Incidence than in the Placebo-Treated Patients in the Adult Short-term Monotherapy Bipolar Depression Study
 | Percentage of Patients Reporting Reaction
Body System or Organ Class Dictionary-derived Term | Placebo (N=168) (%) | LATUDA 20-60 mg/day (N=164) (%) |  | LATUDA 80-120 mg/day (N=167) (%) |  | All LATUDA (N=331) (%)
Gastrointestinal Disorders
Nausea | 8 | 10 | 17 |  | 14
Dry Mouth | 4 | 6 | 4 |  | 5
Vomiting | 2 | 2 | 6 |  | 4
Diarrhea | 2 | 5 | 3 |  | 4
Infections and Infestations
Nasopharyngitis | 1 | 4 | 4 |  | 4
Influenza | 1 | <1 | 2 |  | 2
Urinary Tract Infection | <1 | 2 | 1 |  | 2
Musculoskeletal and Connective Tissue
Disorders
Back Pain | <1 | 3 | <1 |  | 2
Nervous System Disorders
Extrapyramidal Symptoms* | 2 | 5 | 9 |  | 7
Akathisia | 2 | 8 | 11 |  | 9
Somnolence** | 7 | 7 | 14 |  | 11
Psychiatric Disorders
Anxiety | 1 | 4 | 5 |  | 4
Note: Figures rounded to the nearest integer
*Extrapyramidal symptoms include adverse event terms: bradykinesia, cogwheel rigidity, drooling, dystonia, extrapyramidal disorder, glabellar reflex abnormal, hypokinesia, muscle rigidity, oculogyric crisis, oromandibular dystonia, parkinsonism, psychomotor retardation, tongue spasm, torticollis, tremor, and trismus
** Somnolence includes adverse event terms: hypersomnia, hypersomnolence, sedation, and somnolence

Dose-Related Adverse Reactions in the Monotherapy Study:

In the adult short-term, placebo-controlled study (involving lower and higher LATUDA dose ranges) [see Clinical Studies (14.2)] the adverse reactions that occurred with a greater than 5% incidence in the patients treated with LATUDA in any dose group and greater than placebo in both groups were nausea (10.4%, 17.4%), somnolence (7.3%, 13.8%), akathisia (7.9%, 10.8%), and extrapyramidal symptoms (4.9%, 9.0%) for LATUDA 20 to 60 mg/day and LATUDA 80 to 120 mg/day, respectively.

Bipolar Depression

Adjunctive Therapy with Lithium or Valproate

The following findings are based on two adult short-term, placebo-controlled premarketing studies for bipolar depression in which LATUDA was administered at daily doses ranging from 20 to 120 mg as adjunctive therapy with lithium or valproate (n=360).

Commonly Observed Adverse Reactions: The most common adverse reactions (incidence ≥5% and at least twice the rate of placebo) in subjects treated with LATUDA were akathisia and somnolence.

Adverse Reactions Associated with Discontinuation of Treatment: A total of 5.8% (21/360) LATUDA-treated patients and 4.8% (16/334) of placebo-treated patients discontinued due to adverse reactions. There were no adverse reactions associated with discontinuation in subjects treated with LATUDA that were at least 2% and at least twice the placebo rate.

Adverse Reactions Occurring at an Incidence of 2% or More in LATUDA-Treated Patients: Adverse reactions associated with the use of LATUDA (incidence of 2% or greater, rounded to the nearest percent and LATUDA incidence greater than placebo) that occurred during acute therapy (up to 6 weeks in patients with bipolar depression) are shown in Table 21.

Table 21: Adverse Reactions in 2% or More of LATUDA-Treated Patients and That Occurred at Greater Incidence than in the Placebo-Treated Patients in the Adult Short-term Adjunctive Therapy Bipolar Depression Studies
 |  | Percentage of Patients Reporting Reaction
Body System or Organ Class Dictionary-derived Term |  | Placebo (N=334) (%) |  | LATUDA 20 to 120 mg/day (N=360) (%)
Gastrointestinal Disorders
Nausea |  | 10 |  | 14
Vomiting |  | 1 |  | 4
General Disorders
Fatigue |  | 1 |  | 3
Infections and Infestations
Nasopharyngitis |  | 2 |  | 4
Investigations
Weight Increased |  | <1 |  | 3
Metabolism and Nutrition Disorders
Increased Appetite |  | 1 |  | 3
Nervous System Disorders
Extrapyramidal Symptoms* |  | 9 |  | 14
Somnolence** |  | 5 |  | 11
Akathisia |  | 5 |  | 11
Psychiatric Disorders
Restlessness |  | <1 |  | 4
Note: Figures rounded to the nearest integer
*Extrapyramidal symptoms include adverse event terms: bradykinesia, cogwheel rigidity, drooling, dystonia, extrapyramidal disorder, glabellar reflex abnormal, hypokinesia, muscle rigidity, oculogyric crisis, oromandibular dystonia, parkinsonism, psychomotor retardation, tongue spasm, torticollis, tremor, and trismus
** Somnolence includes adverse event terms: hypersomnia, hypersomnolence, sedation, and somnolence

Adolescents

Schizophrenia

The following findings are based on the short-term, placebo-controlled adolescent study for schizophrenia in which LATUDA was administered at daily doses ranging from 40 (N=110) to 80 mg (N=104).

Commonly Observed Adverse Reactions: The most common adverse reactions (incidence ≥5% and at least twice the rate of placebo) in adolescent patients (13 to 17 years) treated with LATUDA were somnolence, nausea, akathisia, extrapyramidal symptoms (non-akathisia, 40 mg only), vomiting, and rhinorrhea/rhinitis (80 mg only).

Adverse Reactions Associated with Discontinuation of Treatment: The incidence of discontinuation due to adverse reactions between LATUDA- and placebo-treated adolescent patients (13 to 17 years) was 4% and 8%, respectively.

Adverse Reactions Occurring at an Incidence of 2% or More in LATUDA-Treated Patients: Adverse reactions associated with the use of LATUDA (incidence of 2% or greater, rounded to the nearest percent and LATUDA incidence greater than placebo) that occurred during acute therapy (up to 6-weeks in adolescent patients with schizophrenia) are shown in Table 22.

Table 22: Adverse Reactions in 2% or More of LATUDA-Treated Patients and That Occurred at Greater Incidence than in the Placebo-Treated Patients in the Adolescent Short-term Schizophrenia Study
 | Percentage of Patients Reporting Reaction
Body System or Organ Class Dictionary-derived Term | Placebo (N=112) | LATUDA 40 mg/day (N=110) | LATUDA 80 mg/day (N=104) | All LATUDA (N=214)
Gastrointestinal Disorders
Nausea | 3 | 13 | 14 | 14
Vomiting | 2 | 8 | 6 | 8
Diarrhea | 1 | 3 | 5 | 4
Dry Mouth | 0 | 2 | 3 | 2
Infections and Infestations
Viral Infection** | 6 | 11 | 10 | 10
Rhinitis*** | 2 | <1 | 8 | 4
Oropharyngeal pain | 0 | <1 | 3 | 2
Tachycardia | 0 | 0 | 3 | 1
Nervous System Disorders
Somnolence* | 7 | 15 | 13 | 15
Akathisia | 2 | 9 | 9 | 9
Dizziness | 1 | 5 | 5 | 5
Note: Figures rounded to the nearest integer
* Somnolence includes adverse event terms: hypersomnia, sedation, and somnolence
** Viral Infection includes adverse event terms: nasopharyngitis, influenza, viral infection, upper respiratory tract infection
*** Rhinitis incudes adverse event terms: rhinitis, allergic rhinitis, rhinorrhea, and nasal congestion

Pediatric Patients (10 to 17 years)

Bipolar Depression

The following findings are based on the 6-week, placebo-controlled study for bipolar depression in pediatric patients 10 to 17 years in which LATUDA was administered at daily doses ranging from 20 to 80 mg (N=175).

Commonly Observed Adverse Reactions: The most common adverse reactions (incidence ≥5%, and at least twice the rate of placebo) in pediatric patients (10 to 17 years) treated with LATUDA were nausea, weight increase, and insomnia.

Adverse Reactions Associated with Discontinuation of Treatment: The incidence of discontinuation due to adverse reactions between LATUDA- and placebo-treated pediatric patients 10 to 17 years was 2% and 2%, respectively.

Adverse Reactions Occurring at an Incidence of 2% or More in LATUDA-Treated Patients: Adverse reactions associated with the use of LATUDA (incidence of 2% or greater, rounded to the nearest percent and LATUDA incidence greater than placebo) that occurred during acute therapy (up to 6 weeks in pediatric patients with bipolar depression) are shown in Table 23.

Table 23: Adverse Reactions in 2% or More of LATUDA-Treated Patients and That Occurred at Greater Incidence than in the Placebo-Treated Patients in the 6-Week Bipolar Depression Study in Pediatric Patients (10 to 17 years)
 |  | Percentage of Patients Reporting Reaction
Body System or Organ Class Dictionary-derived Term |  | Placebo (N=172) |  | LATUDA 20 to 80 mg/day (N=175)
Gastrointestinal Disorders
Nausea |  | 6 |  | 16
Vomiting |  | 4 |  | 6
Abdominal Pain Upper |  | 2 |  | 3
Diarrhea |  | 2 |  | 3
Abdominal Pain |  | 1 |  | 3
General Disorders And Administration Site Conditions
Fatigue |  | 2 |  | 3
Investigations
Weight Increased |  | 2 |  | 7
Metabolism and Nutrition Disorders
Decreased Appetite |  | 2 |  | 4
Nervous System Disorders
Somnolence* |  | 6 |  | 11
Extrapyramidal symptoms** |  | 5 |  | 6
Dizziness |  | 5 |  | 6
Psychiatric Disorders
Insomnia |  | 2 |  | 5
Abnormal Dreams |  | 2 |  | 2
Respiratory, Thoracic and Mediastinal Disorders
Oropharyngeal Pain |  | 2 |  | 2
Note: Figures rounded to the nearest integer
*Somnolence includes adverse event terms: hypersomnia, hypersomnolence, sedation, and somnolence
**EPS includes adverse event terms: akathisia, cogwheel rigidity, dyskinesia, dystonia, hyperkinesia, joint stiffness, muscle rigidity, muscle spasms, musculoskeletal stiffness, oculogyric crisis, parkinsonism, tardive dyskinesia, and tremor

Extrapyramidal Symptoms

Schizophrenia

Adults

In the short-term, placebo-controlled schizophrenia studies, for LATUDA-treated patients, the incidence of reported events related to extrapyramidal symptoms (EPS), excluding akathisia and restlessness, was 13.5% and 5.8% for placebo-treated patients. The incidence of akathisia for LATUDA-treated patients was 12.9% and 3.0% for placebo-treated patients. Incidence of EPS by dose is provided in Table 24.

Table 24: Incidence of EPS Compared to Placebo in Adult Schizophrenia Studies
 |  |  | LATUDA
Adverse Event Term | Placebo (N=708) (%) | 20 mg/day (N=71) (%) | 40 mg/day (N=487) (%) | 80 mg/day (N=538) (%) | 120 mg/day (N=291) (%) | 160 mg/day (N=121) (%)
All EPS events | 9 | 10 | 21 | 23 | 39 | 20
All EPS events, excluding Akathisia/Restlessness | 6 | 6 | 11 | 12 | 22 | 13
Akathisia | 3 | 6 | 11 | 12 | 22 | 7
Dystonia* | <1 | 0 | 4 | 5 | 7 | 2
Parkinsonism** | 5 | 6 | 9 | 8 | 17 | 11
Restlessness | 1 | 1 | 3 | 1 | 3 | 2
Note: Figures rounded to the nearest integer
* Dystonia includes adverse event terms: dystonia, oculogyric crisis, oromandibular dystonia, tongue spasm, torticollis, and trismus
** Parkinsonism includes adverse event terms: bradykinesia, cogwheel rigidity, drooling, extrapyramidal disorder, hypokinesia, muscle rigidity, parkinsonism, psychomotor retardation, and tremor

Adolescents

In the short-term, placebo-controlled, study of schizophrenia in adolescents, the incidence of EPS, excluding events related to akathisia, for LATUDA-treated patients was higher in the 40 mg (10%) and the 80 mg (7.7%) treatment groups vs. placebo (3.6%); and the incidence of akathisia-related events for LATUDA-treated patients was 8.9% vs. 1.8% for placebo-treated patients. Incidence of EPS by dose is provided in Table 25.

Table 25: Incidence of EPS Compared to Placebo in the Adolescent Schizophrenia Study
 |  | LATUDA
Adverse Event Term | Placebo (N=112) (%) | 40 mg/day (N=110) (%) | 80 mg/day (N=104) (%)
All EPS events | 5 | 14 | 14
All EPS events, excluding Akathisia/Restlessness | 4 | 7 | 7
Akathisia | 2 | 9 | 9
Parkinsonism** | <1 | 4 | 0
Dyskinesia | <1 | <1 | 1
Dystonia* | 0 | <1 | 1
Note: Figures rounded to the nearest integer
* Dystonia includes adverse event terms: dystonia, trismus, oculogyric crisis, oromandibular dystonia, tongue spasm, and torticollis
** Parkinsonism includes adverse event terms: bradykinesia, drooling, extrapyramidal disorder, glabellar reflex abnormal, hypokinesia, parkinsonism, and psychomotor retardation

Bipolar Depression

Adults

Monotherapy

In the adult short-term, placebo-controlled monotherapy bipolar depression study, for LATUDA-treated patients, the incidence of reported events related to EPS, excluding akathisia and restlessness was 6.9% and 2.4% for placebo-treated patients. The incidence of akathisia for LATUDA-treated patients was 9.4% and 2.4% for placebo-treated patients. Incidence of EPS by dose groups is provided in Table 26.

Table 26: Incidence of EPS Compared to Placebo in the Adult Monotherapy Bipolar Depression Study
 |  |  | LATUDA
Adverse Event Term | Placebo (N=168) (%) |  | 20 to 60 mg/day (N=164) (%) | 80 to 120 mg/day (N=167) (%)
All EPS events | 5 |  | 12 | 20
All EPS events, excluding Akathisia/Restlessness | 2 |  | 5 | 9
Akathisia | 2 |  | 8 | 11
Dystonia* | 0 |  | 0 | 2
Parkinsonism** | 2 |  | 5 | 8
Restlessness | <1 |  | 0 | 3
Note: Figures rounded to the nearest integer
* Dystonia includes adverse event terms: dystonia, oculogyric crisis, oromandibular dystonia, tongue spasm, torticollis, and trismus
** Parkinsonism includes adverse event terms: bradykinesia, cogwheel rigidity, drooling, extrapyramidal disorder, glabellar reflex abnormal, hypokinesia, muscle rigidity, parkinsonism, psychomotor retardation, and tremor

Adjunctive Therapy with Lithium or Valproate

In the adult short-term, placebo-controlled adjunctive therapy bipolar depression studies, for LATUDA-treated patients, the incidence of EPS, excluding akathisia and restlessness, was 13.9% and 8.7% for placebo. The incidence of akathisia for LATUDA-treated patients was 10.8% and 4.8% for placebo-treated patients. Incidence of EPS is provided in Table 27.

Table 27: Incidence of EPS Compared to Placebo in the Adult Adjunctive Therapy Bipolar Depression Studies
Adverse Event Term | Placebo (N=334) (%) | LATUDA 20 to 120 mg/day (N=360) (%)
All EPS events | 13 | 24
All EPS events, excluding Akathisia/Restlessness | 9 | 14
Akathisia | 5 | 11
Dystonia* | <1 | 1
Parkinsonism** | 8 | 13
Restlessness | <1 | 4
Note: Figures rounded to the nearest integer
* Dystonia includes adverse event terms: dystonia, oculogyric crisis, oromandibular dystonia, tongue spasm, torticollis, and trismus
** Parkinsonism includes adverse event terms: bradykinesia, cogwheel rigidity, drooling, extrapyramidal disorder, glabellar reflex abnormal, hypokinesia, muscle rigidity, parkinsonism, psychomotor retardation, and tremor

In the short-term, placebo-controlled schizophrenia and bipolar depression studies, data was objectively collected on the Simpson Angus Rating Scale (SAS) for extrapyramidal symptoms (EPS), the Barnes Akathisia Scale (BAS) for akathisia and the Abnormal Involuntary Movement Scale (AIMS) for dyskinesias.

Pediatric Patients (10 to 17 years)

In the 6-week, placebo-controlled study of bipolar depression in pediatric patients 10 to 17 years, the incidence of EPS, excluding events related to akathisia, for LATUDA-treated patients was similar in the LATUDA 20 to 80 mg/day (3.4%) treatment group vs. placebo (3.5%); and the incidence of akathisia-related events for LATUDA-treated patients was 2.9% vs. 3.5% for placebo-treated patients. Incidence of EPS by dose is provided in Table 28.

Table 28: Incidence of EPS Compared to Placebo in the Bipolar Depression Study in Pediatric Patients (10 to 17 years)
Adverse Event Term | Placebo (N=172) (%) | LATUDA 20 to 80 mg/day (N=175) (%)
All EPS events* | 5 | 6
All EPS events, excluding Akathisia/Restlessness | 4 | 3
Akathisia | 4 | 3
Parkinsonism** | <1 | <1
Dystonia*** | 1 | <1
Salivary hypersecretion | <1 | <1
Psychomotor hyperactivity | 0 | <1
Tardive Dyskinesia | <1 | 0
Note: Figures rounded to the nearest integer
* EPS include adverse event terms: akathisia, cogwheel rigidity, dyskinesia, dystonia, hyperkinesia, joint stiffness, muscle rigidity, muscle spasms, musculoskeletal stiffness, oculogyric crisis, parkinsonism, tardive dyskinesia, and tremor
** Parkinsonism includes adverse event terms: bradykinesia, drooling, extrapyramidal disorder, glabellar reflex abnormal, hypokinesia, parkinsonism, and psychomotor retardation
***Dystonia includes adverse event terms: dystonia, oculogyric crisis, oromandibular dystonia, tongue spasm, torticollis, and trismus

Schizophrenia

Adults

The mean change from baseline for LATUDA-treated patients for the SAS, BAS and AIMS was comparable to placebo-treated patients, with the exception of the Barnes Akathisia Scale global score (LATUDA, 0.1; placebo, 0.0). The percentage of patients who shifted from normal to abnormal was greater in LATUDA-treated patients and placebo for the BAS (LATUDA, 14.4%; placebo, 7.1%), the SAS (LATUDA, 5.0%; placebo, 2.3%) and the AIMS (LATUDA, 7.4%; placebo, 5.8%).

Adolescents

The mean change from baseline for LATUDA-treated patients with adolescent schizophrenia for the SAS, BAS and AIMS was comparable to placebo-treated patients. The percentage of patients who shifted from normal to abnormal was greater in LATUDA-treated patients and placebo for the BAS (LATUDA, 7.0%; placebo, 1.8%), the SAS (LATUDA, 8.3%; placebo, 2.7%) and the AIMS (LATUDA, 2.8%; placebo, 0.9%).

Bipolar Depression

Adults

Monotherapy

The mean change from baseline for LATUDA-treated adult patients for the SAS, BAS and AIMS was comparable to placebo-treated patients. The percentage of patients who shifted from normal to abnormal was greater in LATUDA-treated patients and placebo for the BAS (LATUDA, 8.4%; placebo, 5.6%), the SAS (LATUDA, 3.7%; placebo, 1.9%) and the AIMS (LATUDA, 3.4%; placebo, 1.2%).

Adjunctive Therapy with Lithium or Valproate

The mean change from baseline for LATUDA-treated adult patients for the SAS, BAS and AIMS was comparable to placebo-treated patients. The percentage of patients who shifted from normal to abnormal was greater in LATUDA-treated patients and placebo for the BAS (LATUDA, 8.7%; placebo, 2.1%), the SAS (LATUDA, 2.8%; placebo, 2.1%) and the AIMS (LATUDA, 2.8%; placebo, 0.6%).

Pediatric Patients (10 to 17 years)

The mean change from baseline for LATUDA-treated pediatric patients 10 to 17 years with bipolar depression for the SAS, BAS and AIMS was comparable to placebo-treated patients. The percentage of patients who shifted from normal to abnormal was greater in LATUDA-treated patients and placebo for the BAS (LATUDA, 4.6%; placebo, 2.4%), the SAS (LATUDA, 0.6%; placebo, 0%) and was the same for the AIMS (LATUDA, 0%; placebo, 0%).

Dystonia

Class Effect: Symptoms of dystonia, prolonged abnormal contractions of muscle groups, may occur in susceptible individuals during the first few days of treatment. Dystonic symptoms include: spasm of the neck muscles, sometimes progressing to tightness of the throat, swallowing difficulty, difficulty breathing, and/or protrusion of the tongue. While these symptoms can occur at low doses, they occur more frequently and with greater severity with high potency and at higher doses of first-generation antipsychotic drugs. An elevated risk of acute dystonia is observed in males and younger age groups.

Schizophrenia

Adults

In the short-term, placebo-controlled schizophrenia clinical studies, dystonia occurred in 4.2% of LATUDA-treated subjects (0.0% LATUDA 20 mg, 3.5% LATUDA 40 mg, 4.5% LATUDA 80 mg, 6.5% LATUDA 120 mg and 2.5% LATUDA 160 mg) compared to 0.8% of subjects receiving placebo. Seven subjects (0.5%, 7/1508) discontinued clinical trials due to dystonic events – four were receiving LATUDA 80 mg/day and three were receiving LATUDA 120 mg/day.

Adolescents

In the short-term, placebo-controlled, adolescent schizophrenia study, dystonia occurred in 1% of LATUDA-treated patients (1% LATUDA 40 mg and 1% LATUDA 80 mg) compared to 0% of patients receiving placebo. No patients discontinued the clinical study due to dystonic events.

Bipolar Depression

Adults

Monotherapy

In the adult short-term, flexible-dose, placebo-controlled monotherapy bipolar depression study, dystonia occurred in 0.9% of LATUDA-treated subjects (0.0% and 1.8% for LATUDA 20 to 60 mg/day and LATUDA 80 to 120 mg/day, respectively) compared to 0.0% of subjects receiving placebo. No subject discontinued the clinical study due to dystonic events.

Adjunctive Therapy with Lithium or Valproate

In the adult short-term, flexible-dose, placebo-controlled adjunctive therapy bipolar depression studies, dystonia occurred in 1.1% of LATUDA-treated subjects (20 to 120 mg) compared to 0.6% of subjects receiving placebo. No subject discontinued the clinical study due to dystonic events.

Pediatric Patients (10 to 17 years)

In the 6-week, placebo-controlled bipolar depression study in pediatric patients 10 to 17 years, dystonia occurred in 0.6% of LATUDA-treated patients compared to 1.2% of patients receiving placebo. No patients discontinued the clinical study due to dystonic events.

Other Adverse Reactions Observed During the Premarketing Evaluation of LATUDA

Following is a list of adverse reactions reported by adult patients treated with LATUDA at multiple doses of ≥ 20 mg once daily within the premarketing database of 2905 patients with schizophrenia. The reactions listed are those that could be of clinical importance, as well as reactions that are plausibly drug-related on pharmacologic or other grounds. Reactions listed in Table 19 or those that appear elsewhere in the LATUDA label are not included.

Reactions are further categorized by organ class and listed in order of decreasing frequency according to the following definitions: those occurring in at least 1/100 patients (frequent) (only those not already listed in the tabulated results from placebo-controlled studies appear in this listing); those occurring in 1/100 to 1/1000 patients (infrequent); and those occurring in fewer than 1/1000 patients (rare).

Blood and Lymphatic System Disorders: Infrequent: anemia

Cardiac Disorders: Frequent: tachycardia; Infrequent: AV block 1st degree, angina pectoris, bradycardia

Ear and Labyrinth Disorders: Infrequent: vertigo

Eye Disorders: Frequent: blurred vision

Gastrointestinal Disorders: Frequent: abdominal pain, diarrhea; Infrequent: gastritis

General Disorders and Administrative Site Conditions: Rare: sudden death

Investigations: Frequent: CPK increased

Metabolism and Nutritional System Disorders: Frequent: decreased appetite

Musculoskeletal and Connective Tissue Disorders: Rare: rhabdomyolysis

Nervous System Disorders: Infrequent: cerebrovascular accident, dysarthria

Psychiatric Disorders: Infrequent: abnormal dreams, panic attack, sleep disorder

Renal and Urinary Disorders: Infrequent: dysuria; Rare: renal failure

Reproductive System and Breast Disorders: Infrequent: amenorrhea, dysmenorrhea; Rare: breast enlargement, breast pain, galactorrhea, erectile dysfunction, priapism

Skin and Subcutaneous Tissue Disorders: Frequent: rash, pruritus; Rare: angioedema

Vascular Disorders: Frequent: hypertension

Clinical Laboratory Changes

Schizophrenia

Adults

Serum Creatinine: In short-term, placebo-controlled trials, the mean change from Baseline in serum creatinine was +0.05 mg/dL for LATUDA-treated patients compared to +0.02 mg/dL for placebo-treated patients. A creatinine shift from normal to high occurred in 3.0% (43/1453) of LATUDA-treated patients and 1.6% (11/681) on placebo. The threshold for high creatinine value varied from > 0.79 to > 1.3 mg/dL based on the centralized laboratory definition for each study (Table 29).

Table 29: Serum Creatinine Shifts from Normal at Baseline to High at Study End-Point in Adult Schizophrenia Studies
Laboratory Parameter | Placebo (N=708) | LATUDA 20 mg/day (N=71) | LATUDA 40 mg/day (N=487) | LATUDA 80 mg/day (N=538) | LATUDA 120 mg/day (N=291) | LATUDA 160 mg/day (N=121)
Serum Creatinine Elevated | 2% | 1% | 2% | 2% | 5% | 7%

Adolescents

Serum Creatinine: In the short-term, placebo-controlled, adolescent schizophrenia study, the mean change from Baseline in serum creatinine was –0.009 mg/dL for LATUDA-treated patients compared to +0.017 mg/dL for placebo-treated patients. A creatinine shift from normal to high (based on the centralized laboratory definition) occurred in 7.2% (14/194) of LATUDA-treated patients and 2.9% (3/103) on placebo (Table 30).

Table 30: Serum Creatinine Shifts from Normal at Baseline to High at Study End-Point in the Adolescent Schizophrenia Study
Laboratory Parameter | Placebo (N=103) | LATUDA 40 mg/day (N=97) | LATUDA 80 mg/day (N=97)
Serum Creatinine Elevated | 2.9% | 7.2% | 7.2%

Bipolar Depression

Adults

Monotherapy

Serum Creatinine: In the adult short-term, flexible-dose, placebo-controlled monotherapy bipolar depression study, the mean change from Baseline in serum creatinine was +0.01 mg/dL for LATUDA-treated patients compared to -0.02 mg/dL for placebo-treated patients. A creatinine shift from normal to high occurred in 2.8% (9/322) of LATUDA-treated patients and 0.6% (1/162) on placebo (Table 31).

Table 31: Serum Creatinine Shifts from Normal at Baseline to High at Study End-Point in the Adult Monotherapy Bipolar Depression Study
Laboratory Parameter | Placebo (N=168) | LATUDA 20 to 60 mg/day (N=164) | LATUDA 80 to 120 mg/day (N=167)
Serum Creatinine Elevated | <1% | 2% | 4%

Adjunctive Therapy with Lithium or Valproate

Serum Creatinine: In adult short-term, placebo-controlled premarketing adjunctive studies for bipolar depression, the mean change from Baseline in serum creatinine was +0.04 mg/dL for LATUDA-treated patients compared to -0.01 mg/dL for placebo-treated patients. A creatinine shift from normal to high occurred in 4.3% (15/360) of LATUDA-treated patients and 1.6% (5/334) on placebo (Table 32).

Table 32: Serum Creatinine Shifts from Normal at Baseline to High at Study End-Point in the Adult Adjunctive Therapy Bipolar Depression Studies
Laboratory Parameter | Placebo (N=334) | LATUDA 20 to 120 mg/day (N=360)
Serum Creatinine Elevated | 2% | 4%

Pediatric Patients (10 to 17 years)

Serum Creatinine: In the 6-week, placebo-controlled bipolar depression study in pediatric patients 10 to 17 years, the mean change from Baseline in serum creatinine was +0.021 mg/dL for LATUDA-treated patients compared to +0.009 mg/dL for placebo-treated patients. A creatinine shift from normal to high (based on the centralized laboratory definition) occurred in 6.7% (11/163) of LATUDA-treated patients and 4.5% (7/155) on placebo (Table 33).

Table 33: Serum Creatinine Shifts from Normal at Baseline to High at Study End-Point in the Bipolar Depression Study in Pediatric Patients (10 to 17 years)
Laboratory Parameter | Placebo (N=155) | LATUDA 20 to 80 mg/day (N=163)
Serum Creatinine Elevated | 4.5% | 6.7%

Pediatric Patients (6 to 17 years)

In a 104-week, open-label study in pediatric patients with schizophrenia, bipolar depression, or autistic disorder, the mean change from baseline to Week 104 in serum creatinine was +0.07 mg/dL. In patients with a normal serum creatinine at baseline, 6% experienced a shift to high at endpoint.

6.2 Postmarketing Experience

The following adverse reactions have been identified during postapproval use of LATUDA. Because these reactions are reported voluntarily from a population of uncertain size, it is not always possible to reliably estimate their frequency or establish a causal relationship to drug exposure.

Hypersensitivity Reactions: Urticaria, throat swelling, tongue swelling, dyspnea, and rash.

Metabolism and Nutrition Disorders: Hyponatremia

7 DRUG INTERACTIONS

7.1 Drugs Having Clinically Important Interactions with LATUDA

Table 34: Clinically Important Drug Interactions with LATUDA
Strong CYP3A4 Inhibitors
Clinical Impact: | Concomitant use of LATUDA with strong CYP3A4 inhibitors increased the exposure of lurasidone compared to the use of LATUDA alone [see Clinical Pharmacology (12.3)].
Intervention: | LATUDA should not be used concomitantly with strong CYP3A4 inhibitors [see Contraindications (4)].
Examples: | Ketoconazole, clarithromycin, ritonavir, voriconazole, mibefradil
Moderate CYP3A4 Inhibitors
Clinical Impact: | Concomitant use of LATUDA with moderate CYP3A4 inhibitors increased the exposure of lurasidone compared to the use of LATUDA alone [see Clinical Pharmacology (12.3)].
Intervention: | LATUDA dose should be reduced to half of the original level when used concomitantly with moderate inhibitors of CYP3A4 [see Dosage and Administration (2.6)].
Examples: | Diltiazem, atazanavir, erythromycin, fluconazole, verapamil
Strong CYP3A4 Inducers
Clinical Impact: | Concomitant use of LATUDA with strong CYP3A4 inducers decreased the exposure of lurasidone compared to the use of LATUDA alone [see Clinical Pharmacology (12.3)].
Intervention: | LATUDA should not be used concomitantly with strong CYP3A4 inducers [see Contraindications (4)].
Examples: | Rifampin, avasimibe, St. John's wort, phenytoin, carbamazepine
Moderate CYP3A4 Inducers
Clinical Impact: | Concomitant use of LATUDA with moderate CYP3A4 inducers decreased the exposure of lurasidone compared to the use of LATUDA alone [see Clinical Pharmacology (12.3)].
Intervention: | LATUDA dose should be increased when used concomitantly with moderate inducers of CYP3A4 [see Dosage and Administration (2.6)].
Examples: | Bosentan, efavirenz, etravirine, modafinil, nafcillin

7.2 Drugs Having No Clinically Important Interactions with LATUDA

Based on pharmacokinetic studies, no dosage adjustment of LATUDA is required when administered concomitantly with lithium, valproate, or substrates of P-gp or CYP3A4 [see Clinical Pharmacology (12.3)].

8 USE IN SPECIFIC POPULATIONS

8.1 Pregnancy

Pregnancy Exposure Registry

There is a pregnancy exposure registry that monitors pregnancy outcomes in women exposed to LATUDA during pregnancy. For more information, contact the National Pregnancy Registry for Atypical Antipsychotics at 1-866-961-2388 or visit http://womensmentalhealth.org/clinical-and-research-programs/pregnancyregistry/.

Risk Summary

Neonates exposed to antipsychotic drugs during the third trimester of pregnancy are at risk for extrapyramidal and/or withdrawal symptoms following delivery [see Clinical Considerations]. There are no studies of LATUDA use in pregnant women. The limited available data are not sufficient to inform a drug-associated risk of birth defects or miscarriage. In animal reproduction studies, no teratogenic effects were seen in pregnant rats and rabbits given lurasidone during the period of organogenesis at doses approximately 1.5- and 6-times, the maximum recommended human dose (MRHD) of 160 mg/day, respectively based on mg/m^2 body surface area [see Data].

The estimated background risk of major birth defects and miscarriage for the indicated population(s) is unknown. All pregnancies have a background risk of birth defect, loss or other adverse outcomes. In the U.S. general population, the estimated background risk of major birth defects and miscarriage in clinically recognized pregnancies is 2-4% and 15-20%, respectively.

Clinical Considerations

Fetal/Neonatal Adverse Reactions

Extrapyramidal and/or withdrawal symptoms, including agitation, hypertonia, hypotonia, tremor, somnolence, respiratory distress and feeding disorder have been reported in neonates who were exposed to antipsychotic drugs during the third trimester of pregnancy. These symptoms have varied in severity. Some neonates recovered within hours or days without specific treatment; others required prolonged hospitalization. Monitor neonates for extrapyramidal and/or withdrawal symptoms and manage symptoms appropriately.

Data

Animal Data

Pregnant rats were treated with oral lurasidone at doses of 3, 10, and 25 mg/kg/day during the period of organogenesis. These doses are 0.2, 0.6, and 1.5 times the MRHD of 160 mg/day based on mg/m^2 body surface area. No teratogenic or embryo-fetal effects were observed up to 1.5 times the MRHD of 160 mg/day, based on mg/m^2.

Pregnant rabbits were treated with oral lurasidone at doses of 2, 10, and 50 mg/kg/day during the period of organogenesis. These doses are 0.2, 1.2 and 6 times the MRHD of 160 mg/day based on mg/m^2. No teratogenic or embryo-fetal effects were observed up to 6 times the MRHD of 160 mg/day based on mg/m^2.

Pregnant rats were treated with oral lurasidone at doses of 0.4, 2, and 10 mg/kg/day during the periods of organogenesis and lactation. These doses are 0.02, 0.1 and 0.6 times the MRHD of 160 mg/day based on mg/m^2. No pre- and postnatal developmental effects were observed up to 0.6 times the MRHD of 160 mg/day, based on mg/m^2.

8.2 Lactation

Risk Summary

Lactation studies have not been conducted to assess the presence of lurasidone in human milk, the effects on the breastfed infant, or the effects on milk production. Lurasidone is present in rat milk. The development and health benefits of breastfeeding should be considered along with the mother's clinical need for LATUDA and any potential adverse effects on the breastfed infant from LATUDA or from the underlying maternal condition.

8.4 Pediatric Use

Schizophrenia

The safety and effectiveness of LATUDA 40-mg/day and 80-mg/day for the treatment of schizophrenia in adolescents (13 to 17 years) was established in a 6-week, placebo-controlled clinical study in 326 adolescent patients [see Dosage and Administration (2.1), Adverse Reactions (6.1), and Clinical Studies (14.1)].

The safety and effectiveness of LATUDA has not been established in pediatric patients less than 13 years of age with schizophrenia.

Bipolar Depression

The safety and effectiveness of LATUDA 20 to 80 mg/day for the treatment of bipolar depression in pediatric patients (10 to 17 years) was established in a 6-week, placebo-controlled clinical study in 347 pediatric patients [see Dosage and Administration (2.2), Adverse Reactions (6.1), and Clinical Studies (14.2)].

The safety and effectiveness of LATUDA has not been established in pediatric patients less than 10 years of age with bipolar depression.

Irritability Associated with Autistic Disorder

The effectiveness of LATUDA in pediatric patients for the treatment of irritability associated with autistic disorder has not been established.

Efficacy was not demonstrated in a 6-week study evaluating LATUDA 20 mg/day and 60 mg/day for the treatment of pediatric patients 6 to 17 years of age with irritability associated with autistic disorder diagnosed by Diagnostic and Statistical Manual of Mental Disorders, 4th Ed., Text Revision [DSM-IV-TR] criteria. The primary objective of the study as measured by improvement from Baseline in the irritability subscale of the Aberrant Behavior Checklist (ABC) at Endpoint (Week 6) was not met. A total of 149 patients were randomized to LATUDA or placebo. Vomiting occurred at a higher rate than reported in other LATUDA studies (4/49 or 8% for 20 mg, 14/51 or 27% for 60 mg, and 2/49 or 4% for placebo), particularly in children ages 6 to 12 (13 out of 18 patients on LATUDA with vomiting).

In a long-term, open-label study that enrolled pediatric patients (age 6 to 17 years) with schizophrenia, bipolar depression, or autistic disorder from three short-term, placebo-controlled trials, 54% (378/701) received lurasidone for 104 weeks. There was one adverse event in this trial that was considered possibly drug-related and has not been reported in adults receiving lurasidone: a 10 year old male experienced a prolonged, painful erection, consistent with priapism, that led to treatment discontinuation.

In this trial, the mean increase in height from open-label baseline to Week 104 was 4.94 cm. To adjust for normal growth, z-scores were derived (measured in standard deviations [SD]), which normalize for the natural growth of children and adolescents by comparisons to age- and sex-matched population standards. A z-score change <0.5 SD is considered not clinically significant. In this trial, the mean change in height z-score from open-label baseline to Week 104 was +0.05 SD, indicating minimal deviation from the normal growth curve.

Juvenile animal studies

Adverse effects were seen on growth, physical and neurobehavioral development at doses as low as 0.2 times the MRHD based on mg/m^2. Lurasidone was orally administered to rats from postnatal days 21 through 91 (this period corresponds to childhood, adolescence, and young adulthood in humans) at doses of 3, 30, and 150 (males) or 300 (females) mg/kg/day which are 0.2 to 10 times (males) and 20 times (females) the maximum recommended adult human dose (MRHD) of 160 mg/day based on mg/m^2. The adverse effects included dose-dependent decreases in femoral length, bone mineral content, body and brain weights at 2 times the MRHD in both sexes, and motor hyperactivity at 0.2 and 2 times the MRHD in both sexes based on mg/m^2. In females, there was a delay in attainment of sexual maturity at 2 times the MRHD, associated with decreased serum estradiol. Mortality occurred in both sexes during early post-weaning period and some of the male weanlings died after only 4 treatments at doses as low as 2 times the MRHD based on mg/m^2. Histopathological findings included increased colloid in the thyroids and inflammation of the prostate in males at 10 times MRHD based on mg/m^2 and mammary gland hyperplasia, increased vaginal mucification, and increased ovarian atretic follicles at doses as low as 0.2 times the MRHD based on mg/m^2. Some of these findings were attributed to transiently elevated serum prolactin which was seen in both sexes at all doses. However, there were no changes at any dose level in reproductive parameters (fertility, conception indices, spermatogenesis, estrous cycle, gestation length, parturition, number of pups born). The no effect dose for neurobehavioral changes in males is 0.2 times the MRHD based on mg/m^2 and could not be determined in females. The no effect dose for growth and physical development in both sexes is 0.2 times the MRHD based on mg/m^2.

8.5 Geriatric Use

Clinical studies with LATUDA did not include sufficient numbers of patients aged 65 and older to determine whether or not they respond differently from younger patients. In elderly patients with psychosis (65 to 85), LATUDA concentrations (20 mg/day) were similar to those in young subjects. It is unknown whether dose adjustment is necessary on the basis of age alone.

Elderly patients with dementia-related psychosis treated with LATUDA are at an increased risk of death compared to placebo. LATUDA is not approved for the treatment of patients with dementia-related psychosis [see Boxed Warning, Warnings and Precautions (5.1, 5.3)].

8.6 Renal Impairment

Reduce the maximum recommended dosage in patients with moderate or severe renal impairment (CLcr<50 mL/minute). Patients with impaired renal function (CLcr<50 mL/minute) had higher exposure to lurasidone than patients with normal renal function [see Clinical Pharmacology (12.3)]. Greater exposure may increase the risk of LATUDA-associated adverse reactions [see Dosage and Administration (2.4)].

8.7 Hepatic Impairment

Reduce the maximum recommended dosage in patients with moderate to severe hepatic impairment (Child-Pugh score ≥7). Patients with moderate to severe hepatic impairment (Child-Pugh score ≥7) generally had higher exposure to lurasidone than patients with normal hepatic function [see Clinical Pharmacology (12.3)]. Greater exposure may increase the risk of LATUDA-associated adverse reactions [see Dosage and Administration (2.5)].

8.8 Other Specific Populations

No dosage adjustment for LATUDA is required on the basis of a patient's sex, race, or smoking status [see Clinical Pharmacology (12.3)].

9 DRUG ABUSE AND DEPENDENCE

9.1 Controlled Substance

LATUDA is not a controlled substance.

9.2 Abuse

LATUDA has not been systematically studied in humans for its potential for abuse or physical dependence or its ability to induce tolerance. While clinical studies with LATUDA did not reveal any tendency for drug-seeking behavior, these observations were not systematic and it is not possible to predict the extent to which a CNS-active drug will be misused, diverted and/or abused once it is marketed. Patients should be evaluated carefully for a history of drug abuse, and such patients should be observed carefully for signs of LATUDA misuse or abuse (e.g., development of tolerance, drug-seeking behavior, increases in dose).

10 OVERDOSAGE

10.1 Human Experience

In premarketing clinical studies, accidental or intentional overdosage of LATUDA was identified in one patient who ingested an estimated 560 mg of LATUDA. This patient recovered without sequelae. This patient resumed LATUDA treatment for an additional two months.

10.2 Management of Overdosage

No specific antidotes for LATUDA are known. In managing overdose, provide supportive care, including close medical supervision and monitoring, and consider the possibility of multiple drug involvement. If an overdose occurs, consult a Certified Poison Control Center (1-800-222-1222 or www.poison.org).

Cardiovascular monitoring should commence immediately, including continuous electrocardiographic monitoring for possible arrhythmias. If antiarrhythmic therapy is administered, disopyramide, procainamide, and quinidine carry a theoretical hazard of additive QT-prolonging effects when administered in patients with an acute overdose of LATUDA. Similarly, the alpha-blocking properties of bretylium might be additive to those of LATUDA, resulting in problematic hypotension.

Hypotension and circulatory collapse should be treated with appropriate measures. Epinephrine and dopamine should not be used, or other sympathomimetics with beta-agonist activity, since beta stimulation may worsen hypotension in the setting of LATUDA-induced alpha blockade. In case of severe extrapyramidal symptoms, anticholinergic medication should be administered.

Gastric lavage (after intubation if patient is unconscious) and administration of activated charcoal together with a laxative should be considered.

The possibility of obtundation, seizures, or dystonic reaction of the head and neck following overdose may create a risk of aspiration with induced emesis.

11 DESCRIPTION

LATUDA is an atypical antipsychotic belonging to the chemical class of benzisothiazol derivatives.

Its chemical name is (3aR,4S,7R,7aS)-2-{(1R,2R)-2-[4-(1,2-benzisothiazol-3-yl)piperazin-1-ylmethyl] cyclohexylmethyl}hexahydro-4,7-methano-2H-isoindole-1,3-dione hydrochloride. Its molecular formula is C28H36N4O2S•HCl and its molecular weight is 529.14.

The chemical structure is:

Lurasidone hydrochloride is a white to off-white powder. It is very slightly soluble in water, practically insoluble or insoluble in 0.1 N HCl, slightly soluble in ethanol, sparingly soluble in methanol, practically insoluble or insoluble in toluene and very slightly soluble in acetone.

LATUDA tablets are intended for oral administration only. Each tablet contains 20 mg, 40 mg, 60 mg, 80 mg, or 120 mg of lurasidone hydrochloride.

Inactive ingredients are mannitol, pregelatinized starch, croscarmellose sodium, hypromellose, magnesium stearate, Opadry® and carnauba wax. Additionally, the 80 mg tablet contains yellow ferric oxide and FD&C Blue No. 2 Aluminum Lake.

12 CLINICAL PHARMACOLOGY

12.1 Mechanism of Action

The mechanism of action of lurasidone in the treatment of schizophrenia and bipolar depression is unclear. However, its efficacy in schizophrenia and bipolar depression could be mediated through a combination of central dopamine D2 and serotonin Type 2 (5HT2A) receptor antagonism.

12.2 Pharmacodynamics

Lurasidone is an antagonist with high affinity binding at the dopamine D2 receptors (Ki of 1 nM) and the serotonin 5-HT2A (Ki of 0.5 nM) and 5-HT7 (Ki of 0.5 nM) receptors. It also binds with moderate affinity to the human α2C adrenergic receptors (Ki of 11 nM), is a partial agonist at serotonin 5-HT1A (Ki of 6.4 nM) receptors, and is an antagonist at the α2A adrenergic receptors (Ki of 41 nM). Lurasidone exhibits little or no affinity for histamine H1 and muscarinic M1 receptors (IC50 > 1,000 nM).

ECG Changes

The effects of LATUDA on the QTc interval were evaluated in a randomized, double-blind, multiple-dose, parallel-dedicated thorough QT study in 43 patients with schizophrenia or schizoaffective disorder, who were treated with LATUDA doses of 120 mg daily, 600 mg daily and completed the study. The maximum mean (upper 1-sided, 95% CI) increase in baseline-adjusted QTc intervals based on individual correction method (QTcI) was 7.5 (11.7) ms and 4.6 (9.5) ms, for the 120 mg and 600 mg dose groups respectively, observed at 2 to 4 hours after dosing. In this study, there was no apparent dose (exposure)-response relationship.

In short-term, placebo-controlled studies in schizophrenia and bipolar depression, no post-baseline QT prolongations exceeding 500 msec were reported in patients treated with LATUDA or placebo.

12.3 Pharmacokinetics

Adults

The activity of LATUDA is primarily due to the parent drug. The pharmacokinetics of LATUDA is dose-proportional within a total daily dose range of 20 mg to 160 mg. Steady-state concentrations of LATUDA are reached within 7 days of starting LATUDA.

Following administration of 40 mg of LATUDA, the mean (%CV) elimination half-life was 18 (7) hours.

Absorption and Distribution: LATUDA is absorbed and reaches peak serum concentrations in approximately 1-3 hours. It is estimated that 9-19% of an administered dose is absorbed. Following administration of 40 mg of LATUDA, the mean (%CV) apparent volume of distribution was 6173 (17.2) L. LATUDA is highly bound (~99%) to serum proteins.

In a food effect study, LATUDA mean Cmax and AUC were about 3-times and 2-times, respectively, when administered with food compared to the levels observed under fasting conditions. LATUDA exposure was not affected as meal size was increased from 350 to 1000 calories and was independent of meal fat content [see Dosage and Administration (2.3)].

In clinical studies, establishing the safety and efficacy of LATUDA, patients were instructed to take their daily dose with food [see Dosage and Administration (2.3)].

Metabolism and Elimination: LATUDA is metabolized mainly via CYP3A4. The major biotransformation pathways are oxidative N-dealkylation, hydroxylation of norbornane ring, and S-oxidation. LATUDA is metabolized into two active metabolites (ID-14283 and ID-14326) and two major non-active metabolites (ID-20219 and ID-20220). Based on in vitro studies, LATUDA is not a substrate of CYP1A1, CYP1A2, CYP2A6, CYP4A11, CYP2B6, CYP2C8, CYP2C9, CYP2C19, CYP2D6 or CYP2E1 enzymes. Because LATUDA is not a substrate for CYP1A2, smoking is not expected to have an effect on the pharmacokinetics of LATUDA.

Transporter proteins: In vitro studies suggest LATUDA is not a substrate of OATP1B1 or OATP1B3, however, is probably a substrate of P-gp and BCRP. In vitro studies indicate that LATUDA is not expected to inhibit transporters OATP1B1, OATP1B3, OCT1, OCT2, OAT1, OAT3, MATE1, MATE2-K and BSEP at clinically relevant concentrations. LATUDA is not a clinically significant inhibitor of P-gp. However, it may inhibit BCRP.

Total excretion of radioactivity in urine and feces combined was approximately 89%, with about 80% recovered in feces and 9% recovered in urine, after a single dose of [^14C]-labeled LATUDA.

Following administration of 40 mg of LATUDA, the mean (%CV) apparent clearance was 3902 (18.0) mL/min.

Drug Interaction Studies

Effects of other drugs on the exposure of lurasidone are summarized in Figure 1. A population PK analyses concluded that coadministration of lithium 300-2400 mg/day or valproate 300-2000 mg/day with lurasidone for up to 6 weeks has minimal effect on lurasidone exposure.

And the effects of LATUDA on the exposures of other drugs are summarized in Figure 2. A population PK analyses concluded that coadministration of lurasidone has minimal effect on lithium and valproate exposure when it is coadministered with lithium 300-2400 mg/day or valproate 300-2000 mg/day.

Figure 1: Impact of Other Drugs on LATUDA Pharmacokinetics

Figure 2: Impact of LATUDA on Other Drugs

Studies in Specific Populations

The effect of intrinsic patient factors on the pharmacokinetics of LATUDA is presented in Figure 3.

Pediatric Patients

LATUDA exposure (i.e., steady-state Cmax and AUC) in children and adolescent patients (10 to 17 years of age) was generally similar to that in adults across the dose range from 40 to 160 mg, without adjusting for body weight.

Figure 3: Impact of Other Patient Factors on LATUDA Pharmacokinetics

13 NONCLINICAL TOXICOLOGY

13.1 Carcinogenesis, Mutagenesis, Impairment of Fertility

Carcinogenesis: Lurasidone increased incidences of malignant mammary gland tumors and pituitary gland adenomas in female mice orally dosed with 30, 100, 300, or 650 mg/kg/day. The lowest dose produced plasma levels (AUC) approximately equal to those in humans receiving the MRHD of 160 mg/day. No increases in tumors were seen in male mice up to the highest dose tested, which produced plasma levels (AUC) 14 times those in humans receiving the MRHD.

Lurasidone increased the incidence of mammary gland carcinomas in female rats orally dosed at 12 and 36 mg/kg/day: the lowest dose; 3 mg/kg/day is the no-effect dose which produced plasma levels (AUC) 0.4 times those in humans receiving the MRHD. No increases in tumors were seen in male rats up to the highest dose tested, which produced plasma levels (AUC) 6 times those in humans receiving the MRHD.

Proliferative and/or neoplastic changes in the mammary and pituitary glands of rodents have been observed following chronic administration of antipsychotic drugs and are considered to be prolactin-mediated [see Warnings and Precautions (5.7)].

Mutagenesis: Lurasidone did not cause mutation or chromosomal aberration when tested in vitro and in vivo test battery. Lurasidone was negative in the Ames gene mutation test, the Chinese Hamster Lung (CHL) cells, and in the in vivo mouse bone marrow micronucleus test up to 2000 mg/kg which is 61 times the MRHD of 160 mg/day based on mg/m^2 body surface area.

Impairment of Fertility: Estrus cycle irregularities were seen in rats orally administered lurasidone at 1.5, 15 and 150 mg/kg/day for 15 consecutive days prior to mating, during the mating period, and through gestation day 7. No effect was seen at the lowest dose of 0.1 mg/kg which is approximately 0.006 times the MRHD of 160 mg/day based on mg/m^2. Fertility was reduced only at the highest dose, which was reversible after a 14 day drug-free period. The no-effect dose for reduced fertility was approximately equal to the MRHD based on mg/m^2.

Lurasidone had no effect on fertility in male rats treated orally for 64 consecutive days prior to mating and during the mating period at doses up to 9 times the MRHD based on mg/m^2.

14 CLINICAL STUDIES

14.1 Schizophrenia

Adults

The efficacy of LATUDA for the treatment of schizophrenia was established in five short-term (6-week), placebo-controlled studies in adult patients (mean age of 38.4 years, range 18-72) who met DSM-IV criteria for schizophrenia. An active-control arm (olanzapine or quetiapine extended-release) was included in two studies to assess assay sensitivity.

Several instruments were used for assessing psychiatric signs and symptoms in these studies:

1. Positive and Negative Syndrome Scale (PANSS), is a multi-item inventory of general psychopathology used to evaluate the effects of drug treatment in schizophrenia. PANSS total scores may range from 30 to 210.
2. Brief Psychiatric Rating Scale derived (BPRSd), derived from the PANSS, is a multi-item inventory primarily focusing on positive symptoms of schizophrenia, whereas the PANSS includes a wider range of positive, negative and other symptoms of schizophrenia. The BPRSd consists of 18 items rated on a scale of 1 (not present) to 7 (severe). BPRSd scores may range from 18 to 126.
3. The Clinical Global Impression severity scale (CGI-S) is a clinician-rated scale that measures the subject's current illness state on a 1- to 7-point scale.

The endpoint associated with each instrument is change from baseline in the total score to the end of week 6. These changes are then compared to placebo changes for the drug and control groups.

The results of the studies follow:

1. Study 1: In a 6-week, placebo-controlled trial (N=145) involving two fixed doses of LATUDA (40 or 120 mg/day), both doses of LATUDA at Endpoint were superior to placebo on the BPRSd total score, and the CGI-S.
2. Study 2: In a 6-week, placebo-controlled trial (N=180) involving a fixed dose of LATUDA (80 mg/day), LATUDA at Endpoint was superior to placebo on the BPRSd total score, and the CGI-S.
3. Study 3: In a 6-week, placebo- and active-controlled trial (N=473) involving two fixed doses of LATUDA (40 or 120 mg/day) and an active control (olanzapine), both LATUDA doses and the active control at Endpoint were superior to placebo on the PANSS total score, and the CGI-S.
4. Study 4: In a 6-week, placebo-controlled trial (N=489) involving three fixed doses of LATUDA (40, 80 or 120 mg/day), only the 80 mg/day dose of LATUDA at Endpoint was superior to placebo on the PANSS total score, and the CGI-S.
5. Study 5: In a 6-week, placebo- and active-controlled trial (N=482) involving two fixed doses of LATUDA (80 or 160 mg/day) and an active control (quetiapine extended-release), both LATUDA doses and the active control at Endpoint were superior to placebo on the PANSS total score, and the CGI-S.

Thus, the efficacy of LATUDA at doses of 40, 80, 120 and 160 mg/day has been established (Table 35).

Table 35: Primary Efficacy Results for Studies in Adult Patients with Schizophrenia (BPRSd or PANSS Scores)
Study | Treatment Group | Primary Efficacy Measure: BPRSd
Study | Treatment Group | Mean Baseline Score (SD) | LS Mean Change from Baseline (SE) | Placebo-subtracted Differencea (95% CI)
1 | LATUDA (40 mg/day)* | 54.2 (8.8) | -9.4 (1.6) | -5.6 (-9.8, -1.4)
1 | LATUDA (120 mg/day)* | 52.7 (7.6) | -11.0 (1.6) | -6.7 (-11.0, -2.5)
1 | Placebo | 54.7 (8.1) | -3.8 (1.6) | —
2 | LATUDA (80 mg/day)* | 55.1 (6.0) | -8.9 (1.3) | -4.7 (-8.3, -1.1)
2 | Placebo | 56.1 (6.8) | -4.2 (1.4) | —
 |  | Primary Efficacy Measure: PANSS
3 | LATUDA (40 mg/day)* | 96.6 (10.7) | -25.7 (2.0) | -9.7 (-15.3, -4.1)
 | LATUDA (120 mg/day)* | 97.9 (11.3) | -23.6 (2.1) | -7.5 (-13.4, -1.7)
 | Olanzapine (15 mg/day)*b | 96.3 (12.2) | -28.7 (1.9) | -12.6 (-18.2, -7.9)
 | Placebo | 95.8 (10.8) | -16.0 (2.1) | —
4 | LATUDA (40 mg/day) | 96.5 (11.5) | -19.2 (1.7) | -2.1 (-7.0, 2.8)
 | LATUDA (80 mg/day)* | 96.0 (10.8) | -23.4 (1.8) | -6.4 (-11.3, -1.5)
 | LATUDA (120 mg/day) | 96.0 (9.7) | -20.5 (1.8) | -3.5 (-8.4, 1.4)
 | Placebo | 96.8 (11.1) | -17.0 (1.8) | —
5 | LATUDA (80 mg/day)* | 97.7 (9.7) | -22.2 (1.8) | -11.9 (-16.9, -6.9)
 | LATUDA (160 mg/day)* | 97.5 (11.8) | -26.5 (1.8) | -16.2 (-21.2, -11.2)
 | Quetiapine Extended-release (600 mg/day)*b | 97.7 (10.2) | -27.8 (1.8) | -17.5 (-22.5, -12.4)
 | Placebo | 96.6 (10.2) | -10.3 (1.8) | —
SD: standard deviation; SE: standard error; LS Mean: least-squares mean; CI: confidence interval, unadjusted for multiple comparisons.
a Difference (drug minus placebo) in least-squares mean change from baseline.
b Included for assay sensitivity.
* Doses statistically significantly superior to placebo.

Examination of population subgroups based on age (there were few patients over 65), gender and race did not reveal any clear evidence of differential responsiveness.

Adolescents (13-17 years)

The efficacy of LATUDA was established in a 6-week, multicenter, randomized, double-blind, placebo-controlled study of adolescents (13 to 17 years) who met DSM-IV-TR criteria for schizophrenia (N=326). Patients were randomized to one of two fixed-doses of LATUDA (40 or 80 mg/day) or placebo.

The primary rating instrument used to assess psychiatric signs and symptoms was the PANSS. The key secondary instrument was the CGI-S.

For both dose groups, LATUDA was superior to placebo in reduction of PANSS and CGI-S scores at Week 6. On average, the 80 mg/day dose did not provide additional benefit compared to the 40 mg/day dose.

The primary efficacy results are provided in Table 36.

Table 36: Primary Efficacy Results (PANSS Total Score) for the Adolescent Schizophrenia Study
 | Treatment Group | Primary Efficacy Measure: PANSS
 | Treatment Group | Mean Baseline Score (SD) | LS Mean Change from Baseline (SE) | Placebo-subtracted Differencea (95% CI)
 | LATUDA (40 mg/day)* | 94.5 (10.97) | -18.6 (1.59) | -8.0 (-12.4, -3.7)
 | LATUDA (80 mg/day)* | 94.0 (11.12) | -18.3 (1.60) | -7.7 (-12.1, -3.4)
 | Placebo | 92.8 (11.08) | -10.5 (1.59) | —
SD: standard deviation; SE: standard error; LS Mean: least-squares mean; CI: confidence interval, unadjusted for multiple comparisons.
a Difference (drug minus placebo) in least-squares mean change from baseline.
* Doses statistically significantly superior to placebo.

14.2 Depressive Episodes Associated with Bipolar I Disorder

Adults

Monotherapy

The efficacy of LATUDA, as monotherapy, was established in a 6-week, multicenter, randomized, double-blind, placebo-controlled study of adult patients (mean age of 41.5 years, range 18 to 74) who met DSM-IV-TR criteria for major depressive episodes associated with bipolar I disorder, with or without rapid cycling, and without psychotic features (N=485). Patients were randomized to one of two flexible-dose ranges of LATUDA (20 to 60 mg/day, or 80 to 120 mg/day) or placebo.

The primary rating instrument used to assess depressive symptoms in this study was the Montgomery-Asberg Depression Rating Scale (MADRS), a 10-item clinician-rated scale with total scores ranging from 0 (no depressive features) to 60 (maximum score). The primary endpoint was the change from baseline in MADRS score at Week 6. The key secondary instrument was the Clinical Global Impression-Bipolar-Severity of Illness scale (CGI-BP-S), a clinician-rated scale that measures the subject's current illness state on a 7-point scale, where a higher score is associated with greater illness severity.

For both dose groups, LATUDA was superior to placebo in reduction of MADRS and CGI-BP-S scores at Week 6. The primary efficacy results are provided in Table 37. The high dose range (80 to 120 mg per day) did not provide additional efficacy on average, compared to the low dose range (20 to 60 mg per day).

Adjunctive Therapy with Lithium or Valproate

The efficacy of LATUDA, as an adjunctive therapy with lithium or valproate, was established in a 6-week, multicenter, randomized, double-blind, placebo-controlled study of adult patients (mean age of 41.7 years, range 18 to 72) who met DSM-IV-TR criteria for major depressive episodes associated with bipolar I disorder, with or without rapid cycling, and without psychotic features (N=340). Patients who remained symptomatic after treatment with lithium or valproate were randomized to flexibly dosed LATUDA 20 to 120 mg/day or placebo.

The primary rating instrument used to assess depressive symptoms in this study was the MADRS. The primary endpoint was the change from baseline in MADRS score at Week 6. The key secondary instrument was the CGI-BP-S scale.

LATUDA was superior to placebo in reduction of MADRS and CGI-BP-S scores at Week 6, as an adjunctive therapy with lithium or valproate (Table 37).

Table 37: Primary Efficacy Results for Adult Studies in Depressive Episodes Associated with Bipolar I Disorder (MADRS Scores)
Study | Treatment Group | Primary Efficacy Measure: MADRS
Study | Treatment Group | Mean Baseline Score (SD) | LS Mean Change from Baseline (SE) | Placebo-subtracted Differencea (95% CI)
Monotherapy study | LATUDA (20-60 mg/day)* | 30.3 (5.0) | -15.4 (0.8) | -4.6 (-6.9, -2.3)
Monotherapy study | LATUDA (80-120 mg/day)* | 30.6 (4.9) | -15.4 (0.8) | -4.6 (-6.9, -2.3)
Monotherapy study | Placebo | 30.5 (5.0) | -10.7 (0.8) | —
Adjunctive Therapy study | LATUDA (20-120 mg/day)* + lithium or valproate | 30.6 (5.3) | -17.1 (0.9) | -3.6 (-6.0, -1.1)
Adjunctive Therapy study | Placebo + lithium or valproate | 30.8 (4.8) | -13.5 (0.9) | —
SD: standard deviation; SE: standard error; LS Mean: least-squares mean; CI: confidence interval, unadjusted for multiple comparisons.
a Difference (drug minus placebo) in least-squares mean change from baseline. * Treatment group statistically significantly superior to placebo.

Pediatric Patients (10 to 17 years)

The efficacy of LATUDA was established in a 6-week, multicenter, randomized, double-blind, placebo-controlled study of pediatric patients (10 to 17 years) who met DSM-5 criteria for a major depressive episode associated with bipolar I disorder, with or without rapid cycling, and without psychotic features (N=343). Patients were randomized to flexibly dosed LATUDA 20 to 80 mg/day or placebo. At the end of the clinical study, most patients (67%) received 20 mg/day or 40 mg/day.

The primary rating scale used to assess depressive symptoms in this study was the Children's Depression Rating Scale, Revised (CDRS-R) total score. The CDRS-R is a 17-item clinician-rated scale with total scores ranging from 17 to 113. The primary endpoint was the change from baseline in CDRS-R score at Week 6. The key secondary endpoint was the change from baseline in CGI-BP-S depression score.

LATUDA was superior to placebo in reduction of CDRS-R total score and CGI-BP-S depression score at Week 6. The primary efficacy results are provided in Table 38.

Table 38: Primary Efficacy Results for the Study in Depressive Episodes Associated with Bipolar I Disorder (CDRS-R Total Score) in Pediatric Patients (10 to 17 years)
 | Treatment Group | Primary Efficacy Measure: CDRS-R
 | Treatment Group | Mean Baseline Score (SD) | LS Mean Change from Baseline (SE) | Placebo-subtracted Differencea (95% CI)
 | LATUDA (20 to 80 mg/day)* | 59.2 (8.24) | -21.0 (1.06) | -5.7 (-8.4, -3.0)
 | Placebo | 58.6 (8.26) | -15.3 (1.08) | —
SD: standard deviation; SE: standard error; LS Mean: least-squares mean; CI: confidence interval, unadjusted for multiple comparisons.
a Difference (drug minus placebo) in least-squares mean change from baseline.
* Treatment group statistically significantly superior to placebo.

16 HOW SUPPLIED/STORAGE AND HANDLING

LATUDA tablets are white to off-white, round (20 mg or 40 mg), white to off-white, oblong (60 mg), pale green, oval (80 mg) or white to off-white, oval (120 mg) and identified with strength-specific one-sided debossing, “L20” (20 mg), “L40” (40 mg), “L80” (80 mg) or “L120” (120 mg). Tablets are supplied in the following strengths and package configurations (Table 39).

Table 39: Package Configuration for LATUDA Tablets
Tablet Strength | Package Configuration | NDC Code
20 mg | Bottles of 30 | 63402-302-30
20 mg | Bottles of 90 | 63402-302-90
20 mg | Bottles of 500 | 63402-302-50
20 mg | Box of 100 (Hospital Unit Dose) 10 blister cards, 10 tablets each | 63402-302-10 Carton 63402-302-01 Blister
40 mg | Bottles of 30 | 63402-304-30
40 mg | Bottles of 90 | 63402-304-90
40 mg | Bottles of 500 | 63402-304-50
40 mg | Box of 100 (Hospital Unit Dose) 10 blister cards, 10 tablets each | 63402-304-10 Carton 63402-304-01 Blister
60 mg | Bottles of 30 | 63402-306-30
60 mg | Bottles of 90 | 63402-306-90
60 mg | Bottles of 500 | 63402-306-50
60 mg | Box of 100 (Hospital Unit Dose) 10 blister cards, 10 tablets each | 63402-306-10 Carton 63402-306-01 Blister
80 mg | Bottles of 30 | 63402-308-30
80 mg | Bottles of 90 | 63402-308-90
80 mg | Bottles of 500 | 63402-308-50
80 mg | Box of 100 (Hospital Unit Dose) 10 blister cards, 10 tablets each | 63402-308-10 Carton 63402-308-01 Blister
120 mg | Bottles of 30 | 63402-312-30
120 mg | Bottles of 90 | 63402-312-90
120 mg | Bottles of 500 | 63402-312-50
120 mg | Box of 100 (Hospital Unit Dose) 10 blister cards, 10 tablets each | 63402-312-10 Carton 63402-312-01 Blister

Storage

Store LATUDA tablets at 25°C (77°F); excursions permitted to 15° - 30°C (59° - 86°F) [See USP Controlled Room Temperature].

17 PATIENT COUNSELING INFORMATION

Advise the patient to read the FDA-approved patient labeling (Medication Guide).

Suicidal Thoughts and Behavior

Advise patients and caregivers to look for the emergence of suicidality, especially early during treatment and when the dosage is adjusted up or down and instruct them to report such symptoms to the healthcare provider [see Boxed Warning, Warnings and Precautions (5.2)].

Neuroleptic Malignant Syndrome

Counsel patients about a potentially fatal adverse reaction referred to as Neuroleptic Malignant Syndrome (NMS). Advise patients, family members, or caregivers to contact the healthcare provider or to report to the emergency room if they experience signs and symptoms of NMS [see Warnings and Precautions (5.4)].

Tardive Dyskinesia

Counsel patients on the signs and symptoms of tardive dyskinesia and to contact their healthcare provider if these abnormal movements occur [see Warnings and Precautions (5.5)].

Metabolic Changes

Educate patients about the risk of metabolic changes, how to recognize symptoms of hyperglycemia and diabetes mellitus, and the need for specific monitoring, including blood glucose, lipids, and weight [see Warnings and Precautions (5.6)].

Hyperprolactinemia

Counsel patients on signs and symptoms of hyperprolactinemia that may be associated with chronic use of LATUDA. Advise them to seek medical attention if they experience any of the following: amenorrhea or galactorrhea in females, erectile dysfunction or gynecomastia in males [see Warnings and Precautions (5.7)].

Leukopenia/Neutropenia

Advise patients with a pre-existing low WBC or a history of drug-induced leukopenia/neutropenia that they should have their CBC monitored while taking LATUDA [see Warnings and Precautions (5.8)].

Orthostatic Hypotension

Educate patients about the risk of orthostatic hypotension, particularly at the time of initiating treatment, re-initiating treatment, or increasing the dose [see Warnings and Precautions (5.9)].

Interference with Cognitive and Motor Performance

Caution patients about performing activities requiring mental alertness, such as operating hazardous machinery or operating a motor vehicle, until they are reasonably certain that LATUDA therapy does not affect them adversely [see Warnings and Precautions (5.12)].

Heat Exposure and Dehydration

Educate patients regarding appropriate care in avoiding overheating and dehydration [see Warnings and Precautions (5.13)].

Activation of Mania or Hypomania

Advise patients and their caregivers to observe for signs of activation of mania/hypomania [see Warnings and Precautions (5.14)].

Concomitant Medication

Advise patients to inform their physicians if they are taking, or plan to take, any prescription or over-the-counter drugs, because there is a potential for drug interactions [see Drug Interactions (7)].

Pregnancy

Advise patients that LATUDA may cause extrapyramidal and/or withdrawal symptoms in a neonate. Advise patients to notify their healthcare provider with a known or suspected pregnancy [see Use in Specific Populations (8.1)]. Advise patients that there is a pregnancy exposure registry that monitors pregnancy outcomes in women exposed to LATUDA during pregnancy [see Use in Specific Populations (8.1)].

Sumitomo Pharma
Manufactured for:
Sumitomo Pharma America, Inc.
Marlborough, MA 01752 USA

For Customer Service, call 1-888-394-7377.
For Medical Information, call 1-800-739-0565.
To report suspected adverse reactions, call 1-877-737-7226.

LATUDA is a registered trademark of Sumitomo Pharma Co. Ltd.
Sumitomo Pharma America, Inc. is a U.S. subsidiary of Sumitomo Pharma Co. Ltd.
©2025 Sumitomo Pharma America, Inc.

MEDICATION GUIDE
LATUDA (luh-TOO-duh)
(lurasidone hydrochloride)
tablets

What is the most important information I should know about LATUDA?
LATUDA may cause serious side effects, including:

- Increased risk of death in elderly people with dementia-related psychosis. Medicines like LATUDA can raise the risk of death in elderly people who have lost touch with reality (psychosis) due to confusion and memory loss (dementia). LATUDA is not approved for the treatment of people with dementia-related psychosis.
- Increased risk of suicidal thoughts or actions in children and young adults. Antidepressant medicines may increase suicidal thoughts or actions in some children and young adults within the first few months of treatment and when the dose is changed.
  - Depression and other serious mental illnesses are the most important causes of suicidal thoughts and actions. Some people may have a particularly high risk of having suicidal thoughts or actions. These include people who have (or have a family history of) depression, bipolar illness (also called manic-depressive illness), or a history of suicidal thoughts or actions.
  How can I watch for and try to prevent suicidal thoughts and actions in myself or a family member?
  - Pay close attention to any changes, especially sudden changes in mood, behaviors, thoughts, or feelings. This is very important when an antidepressant medicine is started or when the dose is changed.
  - Call the healthcare provider right away to report new or sudden changes in mood, behavior, thoughts, or feelings.
  - Keep all follow-up visits with the healthcare provider as scheduled. Call the healthcare provider between visits as needed, especially if you have concerns about symptoms.
    Call a healthcare provider right away if you or your family member has any of the following symptoms, especially if they are new, worse, or worry you:
    - thoughts about suicide or dying
    - new or worse depression
    - feeling very agitated or restless
    - trouble sleeping (insomnia)
    - acting aggressive, being angry, or violent
    - an extreme increase in activity and talking (mania)
    - attempts to commit suicide
    - new or worse anxiety
    - panic attacks
    - new or worse irritability
    - acting on dangerous impulses
    - other unusual changes in behavior or mood

What is LATUDA?
LATUDA is a prescription medicine used:

- To treat people 13 years of age or older with schizophrenia.
- Alone to treat people 10 years of age and older with depressive episodes that happen with Bipolar I Disorder (bipolar depression).
- With the medicine lithium or valproate to treat adults with depressive episodes that happen with Bipolar I Disorder (bipolar depression).

It is not known if LATUDA is safe and effective in children:

- less than 13 years of age with schizophrenia.
- less than 10 years of age with bipolar depression.
- for the treatment of irritability associated with autistic disorder.

Do not take LATUDA if you are:

- allergic to lurasidone hydrochloride or any of the ingredients in LATUDA. See the end of this Medication Guide for a complete list of ingredients in LATUDA.
- taking certain other medicines called CYP3A4 inhibitors or inducers including ketoconazole, clarithromycin, ritonavir, voriconazole, mibefradil, rifampin, avasimibe, St. John's wort, phenytoin, or carbamazepine. Ask your healthcare provider if you are not sure if you are taking any of these medicines.

Before taking LATUDA, tell your healthcare provider about all of your medical conditions, including if you:

- have or have had heart problems or stroke
- have or have had low or high blood pressure
- have or have had diabetes or high blood sugar, or have a family history of diabetes or high blood sugar.
- have or have had high levels of total cholesterol or triglycerides
- have or have had high prolactin levels
- have or have had low white blood cell count
- have or have had seizures
- have or have had kidney or liver problems
- are pregnant or plan to become pregnant. It is not known if LATUDA will harm your unborn baby. Talk to your healthcare provider about the risk to your unborn baby if you take LATUDA during pregnancy.
  - Tell your healthcare provider if you become pregnant or think you are pregnant during treatment with LATUDA.
  - If you become pregnant during treatment with LATUDA, talk to your healthcare provider about registering with the National Pregnancy Registry for Atypical Antipsychotics. You can register by calling 1-866-961-2388 or go to http://womensmentalhealth.org/clinical-and-researchprograms/pregnancyregistry/.
- are breastfeeding or plan to breastfeed. It is not known if LATUDA passes into your breast milk. Talk to your healthcare provider about the best way to feed your baby during treatment with LATUDA.

Tell your healthcare provider about all the medicines you take, including prescription and over-the-counter medicines, vitamins, and herbal supplements.
LATUDA and other medicines may affect each other causing possible serious side effects. LATUDA may affect the way other medicines work, and other medicines may affect how LATUDA works.
Your healthcare provider can tell you if it is safe to take LATUDA with your other medicines. Do not start or stop any other medicines during treatment with LATUDA without talking to your healthcare provider first.
Know the medicines you take. Keep a list of your medicines to show your healthcare provider and pharmacist when you get a new medicine.

How should I take LATUDA?

- Take LATUDA exactly as your healthcare provider tells you to take it. Do not change the dose or stop taking LATUDA without first talking to your healthcare provider.
- Take LATUDA by mouth, with food (at least 350 calories).
- If you take too much LATUDA, call your healthcare provider or poison control center or go to the nearest hospital emergency room right away.

What should I avoid while taking LATUDA?

- Do not drive, operate heavy machinery, or do other dangerous activities until you know how LATUDA affects you. LATUDA may make you drowsy.
- Avoid eating grapefruit or drinking grapefruit juice during treatment with LATUDA. Grapefruit and grapefruit juice may affect the amount of LATUDA in your blood.
- Do not become too hot or dehydrated during treatment with LATUDA.
  - Do not exercise too much.
  - In hot weather, stay inside in a cool place if possible.
  - Stay out of the sun.
  - Do not wear too much clothing or heavy clothing.
  - Drink plenty of water.

What are the possible side effects of LATUDA?
LATUDA may cause serious side effects, including:

- See “What is the most important information I should know about LATUDA?”
- Stroke (cerebrovascular problems) in elderly people with dementia-related psychosis that can lead to death.
- Neuroleptic malignant syndrome (NMS) a serious condition that can lead to death. Call your healthcare provider or go to the nearest hospital emergency room right away if you have some or all of the following signs and symptoms of NMS:
  - high fever
  - confusion
  - changes in your breathing, heart rate, and blood pressure
  - stiff muscles
  - increased sweating
- Uncontrolled body movements (tardive dyskinesia). LATUDA may cause movements that you cannot control in your face, tongue, or other body parts. Tardive dyskinesia may not go away, even if you stop taking LATUDA. Tardive dyskinesia may also start after you stop taking LATUDA.
- Problems with your metabolism such as:
  - high blood sugar (hyperglycemia) and diabetes. Increases in blood sugar can happen in some people who take LATUDA. Extremely high blood sugar can lead to coma or death. If you have diabetes or risk factors for diabetes (such as being overweight or a family history of diabetes), your healthcare provider should check your blood sugar before you start and during treatment with LATUDA.
    Call your healthcare provider if you have any of these symptoms of high blood sugar during treatment with LATUDA:
    - feel very thirsty
    - feel very hungry
    - feel sick to your stomach
    - need to urinate more than usual
    - feel weak or tired
    - feel confused, or your breath smells fruity
  - increased fat levels (cholesterol and triglycerides) in your blood.
  - weight gain. You and your healthcare provider should check your weight regularly during treatment with LATUDA.
- Increased prolactin levels in your blood (hyperprolactinemia). Your healthcare provider may do blood tests to check your prolactin levels during treatment with LATUDA. Tell your healthcare provider if you have any of the following signs and symptoms of hyperprolactinemia:
  Females:
  - absence of your menstrual cycle
  - secretion of breast milk when you are not breastfeeding
  Males:
  - problems getting or maintaining an erection (erectile dysfunction)
  - enlargement of breasts (gynecomastia)
- Low white blood cell count. Your healthcare provider may do blood tests during the first few months of treatment with LATUDA.
- Decreased blood pressure (orthostatic hypotension). You may feel lightheaded or faint when you rise too quickly from a sitting or lying position.
- Falls. LATUDA may make you sleepy or dizzy, may cause a decrease in your blood pressure when changing position (orthostatic hypotension), and can slow your thinking and motor skills which may lead to falls that can cause fractures or other injuries.
- Seizures (convulsions) Problems controlling your body temperature so that you feel too warm. See “What should I avoid while taking LATUDA?”
  Mania or hypomania (manic episodes) in people with a history of bipolar disorder. Symptoms may include:
  - greatly increased energy
  - racing thoughts
  - unusually grand ideas
  - talking more or faster than usual
  - severe problems sleeping
  - reckless behavior
  - excessive happiness or irritability
- Difficulty swallowing
  The most common side effects of LATUDA include:
- Adults with schizophrenia:
  - sleepiness or drowsiness
  - restlessness and feeling like you need to move around (akathisia)
  - difficulty moving, slow movements, muscle stiffness, or tremor
  - nausea
- Children 13 to 17 years of age with schizophrenia:
  - sleepiness or drowsiness
  - nausea
  - restlessness and feeling like you need to move around (akathisia)
  - difficulty moving, slow movements, muscle stiffness, or tremor
  - runny nose
  - vomiting
- Adults with bipolar depression:
  - restlessness and feeling like you need to move around (akathisia)
  - difficulty moving, slow movements, muscle stiffness, or tremor
  - sleepiness or drowsiness
- Children 10 to 17 years of age with bipolar depression:
  - nausea
  - weight gain
  - problems sleeping (insomnia)

These are not all of the possible side effects of LATUDA.
Call your doctor for medical advice about side effects. You may report side effects to FDA at 1-800-FDA-1088.

How should I store LATUDA?

- Store LATUDA tablets at room temperature between 68°F to 77°F (20°C to 25°C).
- Keep LATUDA and all medicines out of the reach of children.

General information about the safe and effective use of LATUDA.
Medicines are sometimes prescribed for purposes other than those listed in a Medication Guide. Do not use LATUDA for a condition for which it was not prescribed. Do not give LATUDA to other people, even if they have the same symptoms that you have. It may harm them. You can ask your pharmacist or healthcare provider for information about LATUDA that is written for health professionals.

What are the ingredients in LATUDA?
Active ingredient: lurasidone hydrochloride
Inactive ingredients: mannitol, pregelatinized starch, croscarmellose sodium, hypromellose, magnesium stearate, Opadry® and carnauba wax. Additionally, the 80 mg tablet contains yellow ferric oxide and FD&C Blue No. 2 Aluminum Lake
Manufactured for: Sumitomo Pharma America, Inc. Marlborough, MA 01752 USA
LATUDA is a registered trademark of Sumitomo Pharma Co. Ltd.; Sumitomo Pharma America, Inc. is a U.S. subsidiary of Sumitomo Pharma Co. Ltd. ©2025 Sumitomo Pharma America, Inc.
For more information, go to www.LATUDA.com or call 1-888-394-7377.

This Medication Guide has been approved by the U.S. Food and Drug Administration .

Revised: 1/2025

PACKAGE LABEL

PACKAGE LABEL - PRINCIPAL DISPLAY PANEL - 20 mg, 30 Tablet Label

NDC 63402-302-30

30 Tablets

Latuda®

(lurasidone HCl) tablets

20 mg

ATTENTION DISPENSER: Each time Latuda
is dispensed give the patient the accompanying
Medication Guide, also provided at
www.latuda.com or 1-888-394-7377.

Rx Only

Sunovion

PACKAGE LABEL

PACKAGE LABEL - PRINCIPAL DISPLAY PANEL - 40 mg, 30 Tablet Label

NDC 63402-304-30

30 Tablets

Latuda®

(lurasidone HCl) tablets

40 mg

ATTENTION DISPENSER: Each time Latuda
is dispensed give the patient the accompanying
Medication Guide, also provided at
www.latuda.com or 1-888-394-7377.

Rx Only

Sunovion

PACKAGE LABEL

PACKAGE LABEL - PRINCIPAL DISPLAY PANEL - 60 mg, 30 Tablet Label

NDC 63402-306-30

30 Tablets

Latuda®

(lurasidone HCl) tablets

60 mg

ATTENTION DISPENSER: Each time Latuda
is dispensed give the patient the accompanying
Medication Guide, also provided at
www.latuda.com or 1-888-394-7377.

Rx Only

Sunovion

PACKAGE LABEL

PACKAGE LABEL - PRINCIPAL DISPLAY PANEL - 60 mg, 90-ct LABEL

NDC 63402-306-90

90 Tablets

Latuda®

(lurasidone HCl) tablets

60 mg

ATTENTION DISPENSER: Each time Latuda is dispensed give the patient the accompanying Medication Guide, also provided at www.latuda.com or 1-888-394-7377.

Rx Only

Sunovion

PACKAGE LABEL

PACKAGE LABEL - PRINCIPAL DISPLAY PANEL - 60 mg, 500-ct LABEL

NDC 63402-306-50

500 Tablets

Latuda®

(lurasidone HCl) tablets

60 mg

ATTENTION DISPENSER: Each time Latuda is dispensed give the patient the accompanying Medication Guide, also provided at www.latuda.com or 1-888-394-7377.

Rx Only

Sunovion

PACKAGE LABEL - PRINCIPAL DISPLAY PANEL - 60 mg Blister

NDC 63402-306-07

7 Tablets

PROFESSIONAL SAMPLE

NOT FOR SALE OR REIMBURSEMENT

Latuda®

(lurasidone HCl) tablets

60 mg per tablet

Rx only

ATTENTION DISPENSER: Dispense the enclosed Medication Guide to each patient.

Sunovion

PACKAGE LABEL - PRINCIPAL DISPLAY PANEL – 60 mg Carton

NDC 63402-306-70

28 Tablets (4 Cards, 7 Tablets Each)

PROFESSIONAL SAMPLE

NOT FOR SALE OR REIMBURSEMENT

Latuda®

(lurasidone HCl) tablets

60 mg per tablet

Rx only

ATTENTION DISPENSER: Dispense the enclosed Medication Guide to each patient.

Sunovion

PACKAGE LABEL - PRINCIPAL DISPLAY PANEL – 60 mg Blister

NDC 63402-306-01

10 Tablets

Latuda®

(lurasidone HCl) tablets

60 mg

EXP: LOT:

Sunovion Pharmaceuticals Inc.

PACKAGE LABEL

PACKAGE LABEL - PRINCIPAL DISPLAY PANEL - 60 mg, HUD Carton

NDC 63402-306-10

100 Tablets (10 Cards, 10 Tablets Each)

Latuda®

(lurasidone HCl) tablets

60 mg per tablet

ATTENTION DISPENSER: Each time Latuda is dispensed give the patient the accompanying Medication Guide, also provided at www.latuda.com or 1-888-394-7377.

Rx Only

Sunovion

PACKAGE LABEL

PACKAGE LABEL - PRINCIPAL DISPLAY PANEL - 80 mg, 30 Tablet Label

NDC 63402-308-30

30 Tablets

Latuda®

(lurasidone HCl) tablets

80 mg

ATTENTION DISPENSER: Each time Latuda
is dispensed give the patient the accompanying
Medication Guide, also provided at
www.latuda.com or 1-888-394-7377.

Rx Only

Sunovion

PACKAGE LABEL

PACKAGE LABEL - PRINCIPAL DISPLAY PANEL - 120 mg, 30 Tablet Label

NDC 63402-312-30

30 Tablets

Latuda®

(lurasidone HCl) tablets

120 mg

ATTENTION DISPENSER: Each time Latuda
is dispensed give the patient the accompanying
Medication Guide, also provided at
www.latuda.com or 1-888-394-7377.

Rx Only

Sunovion